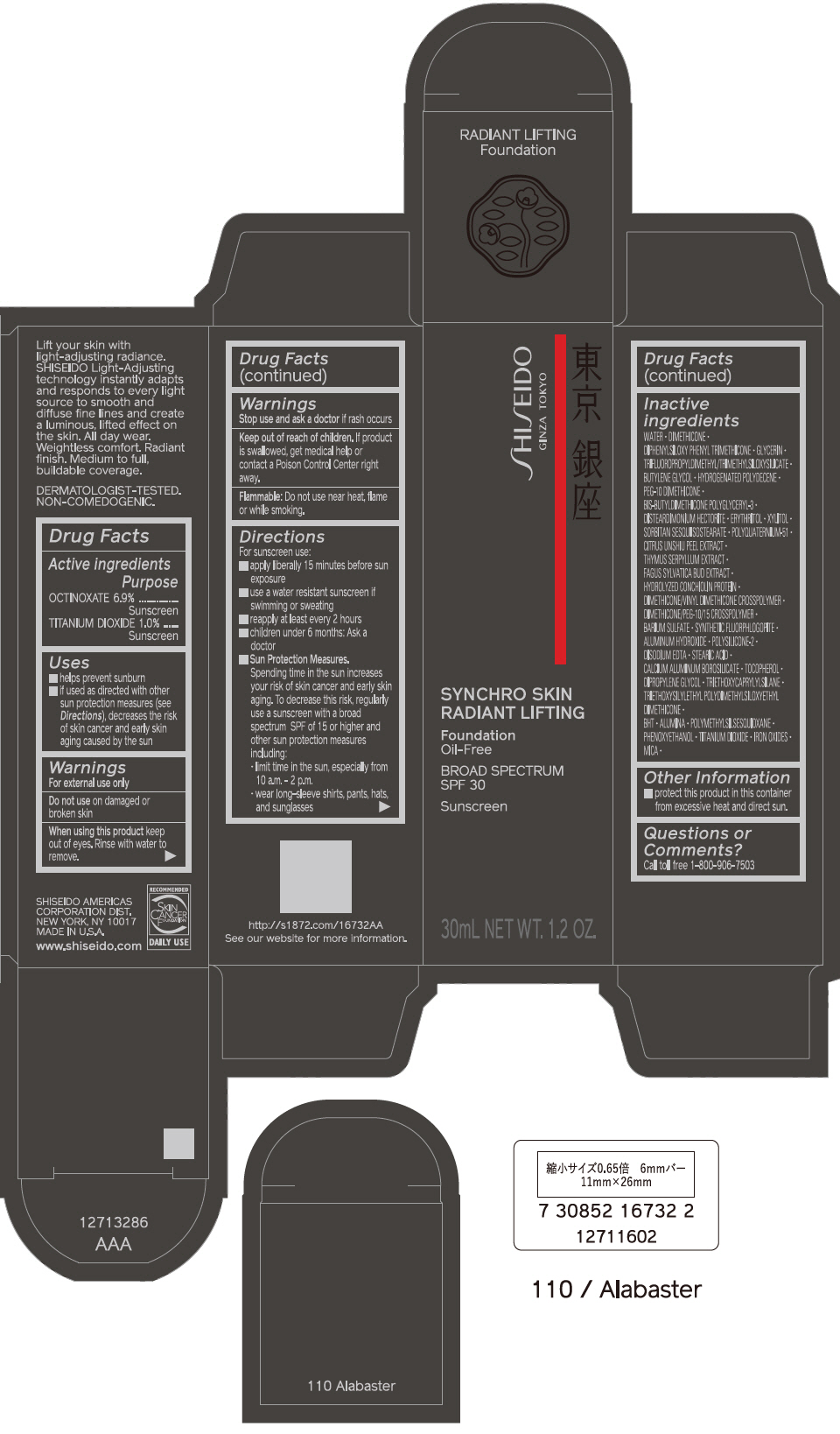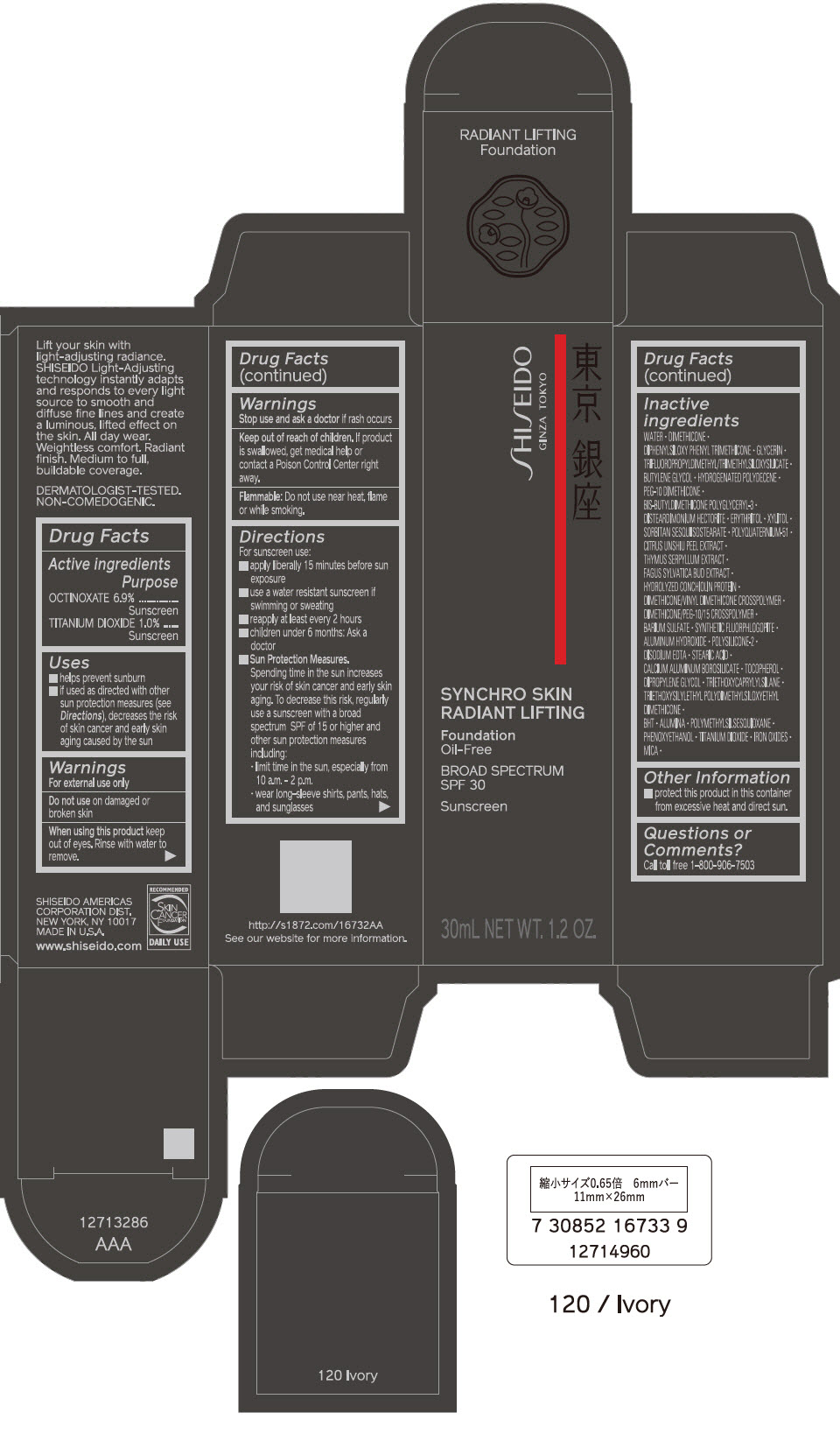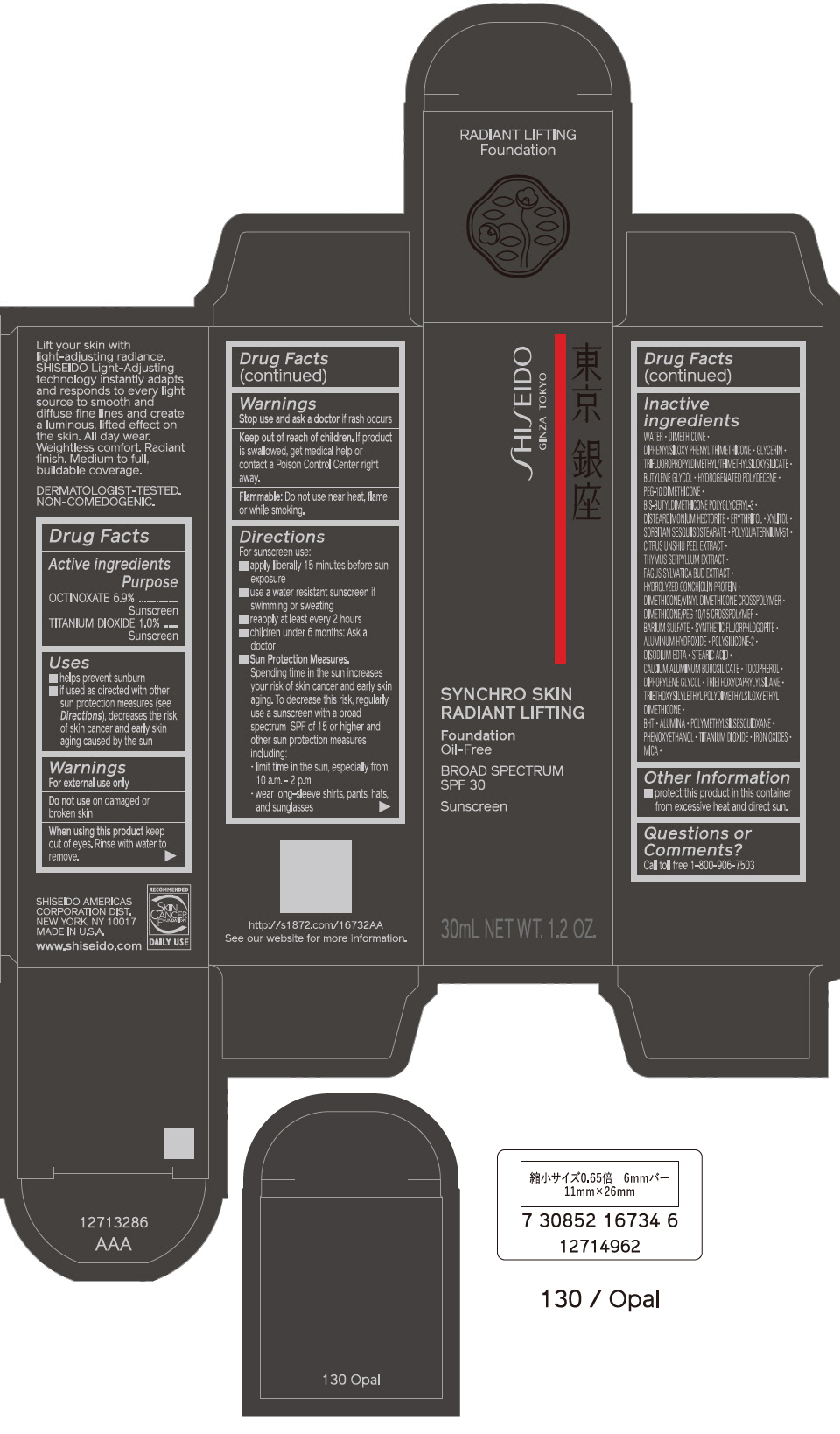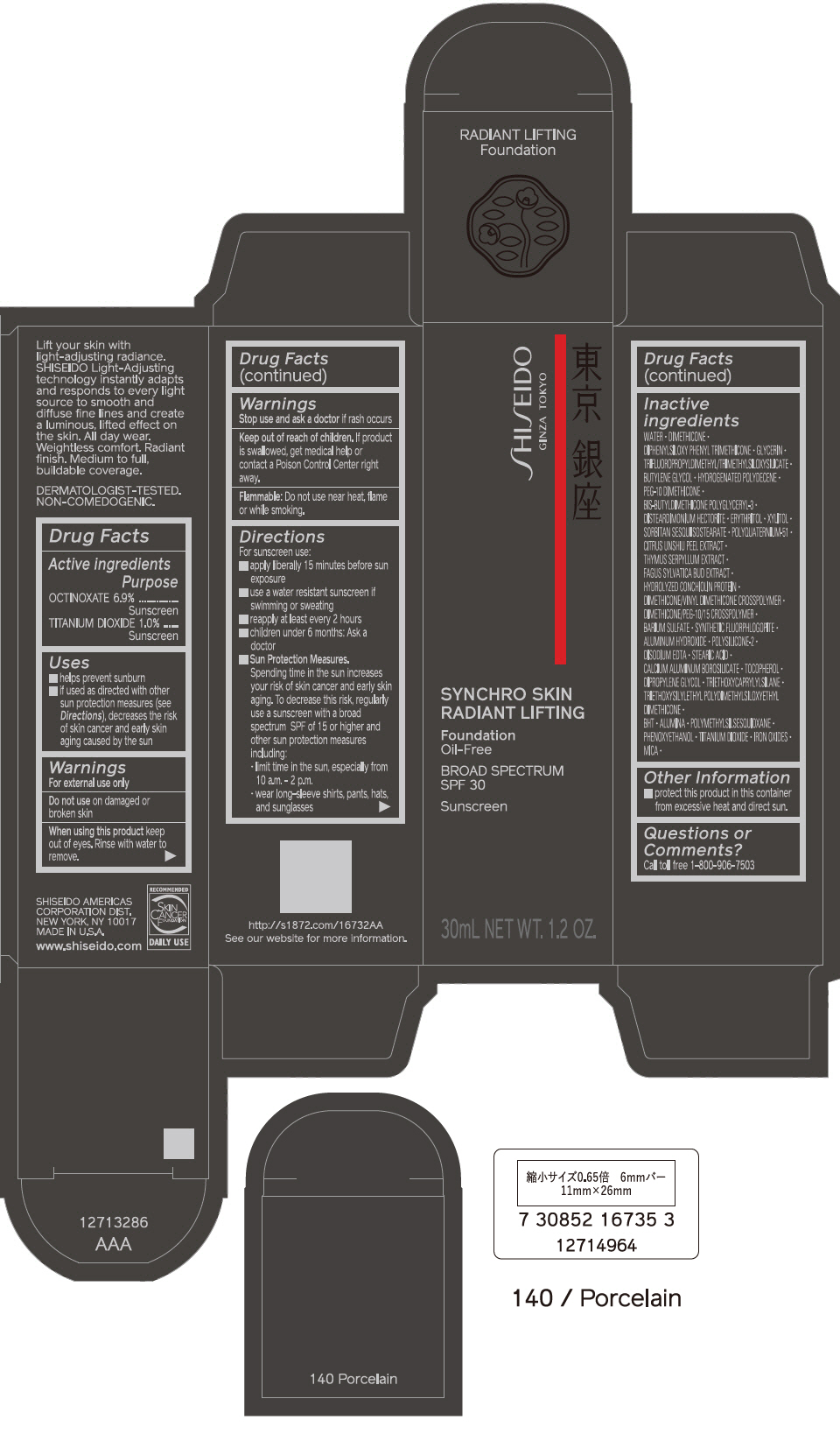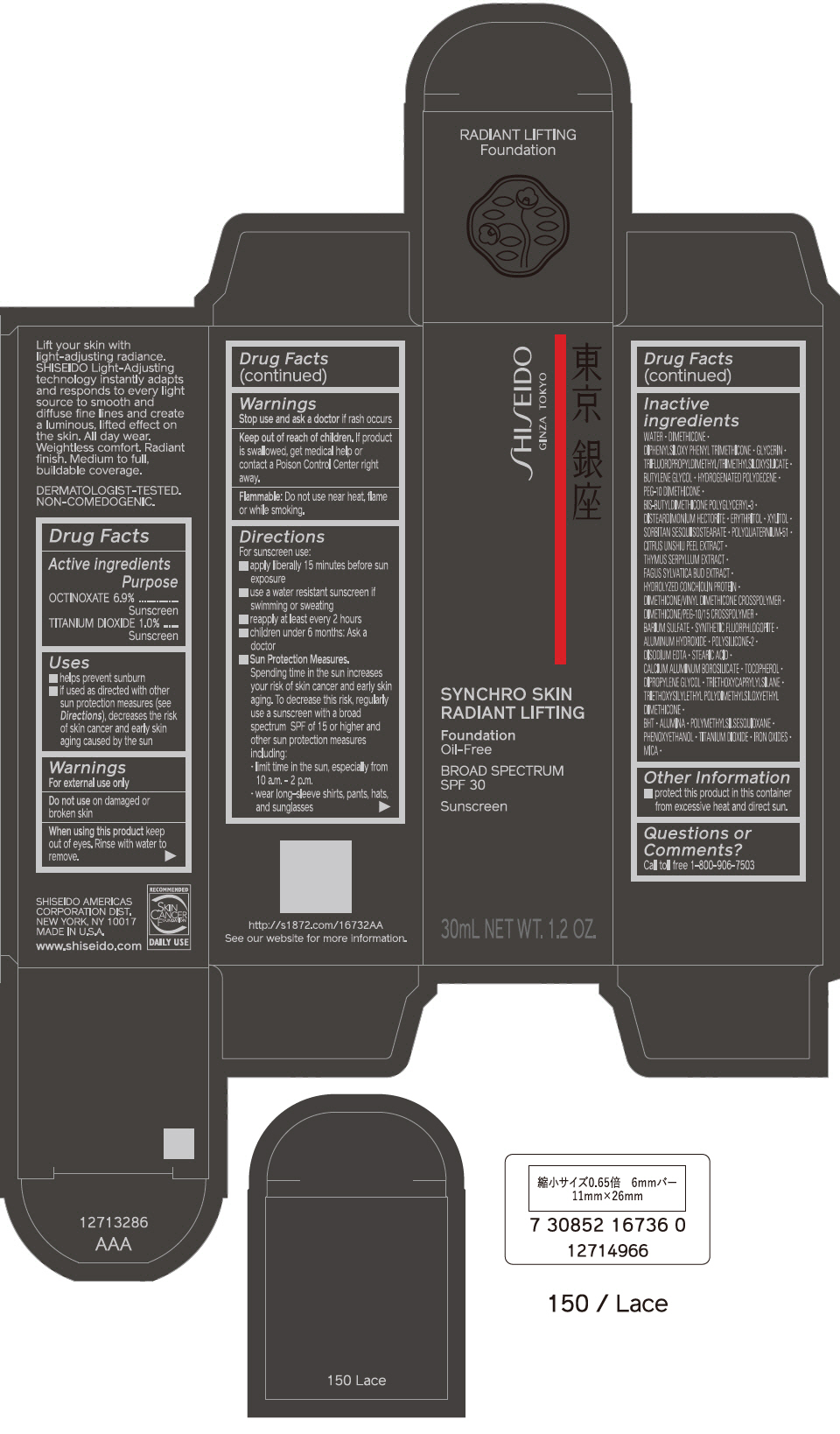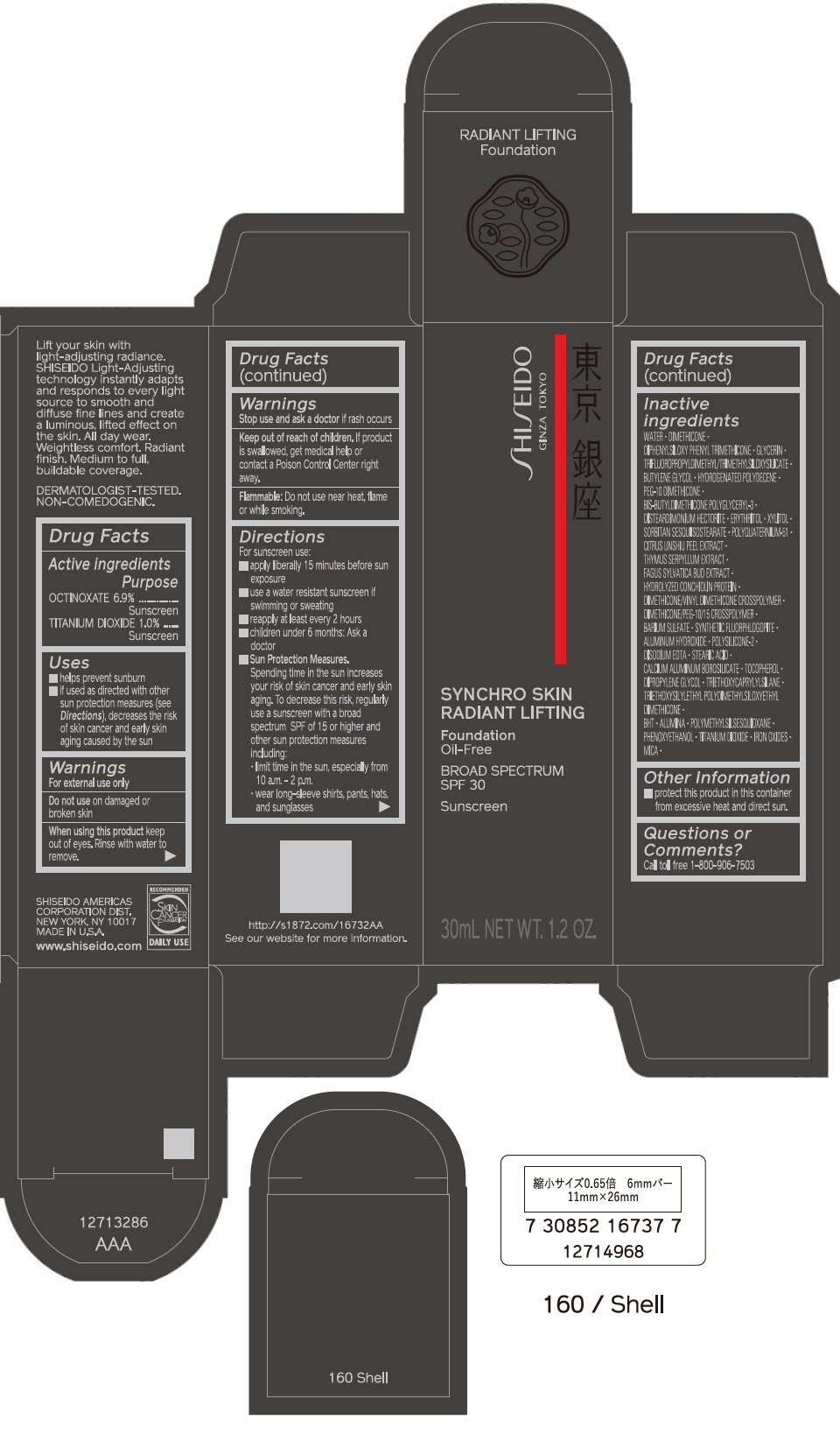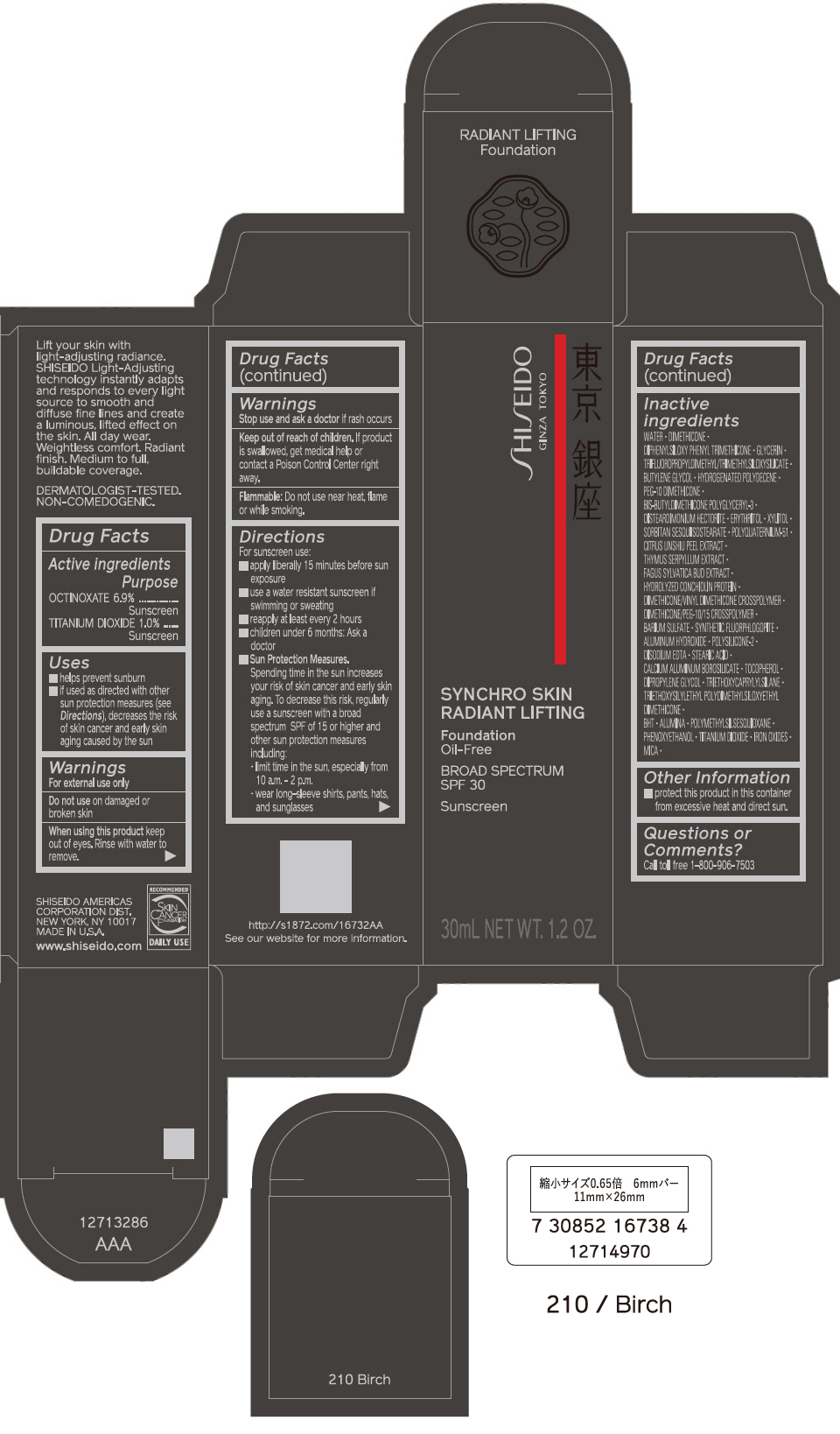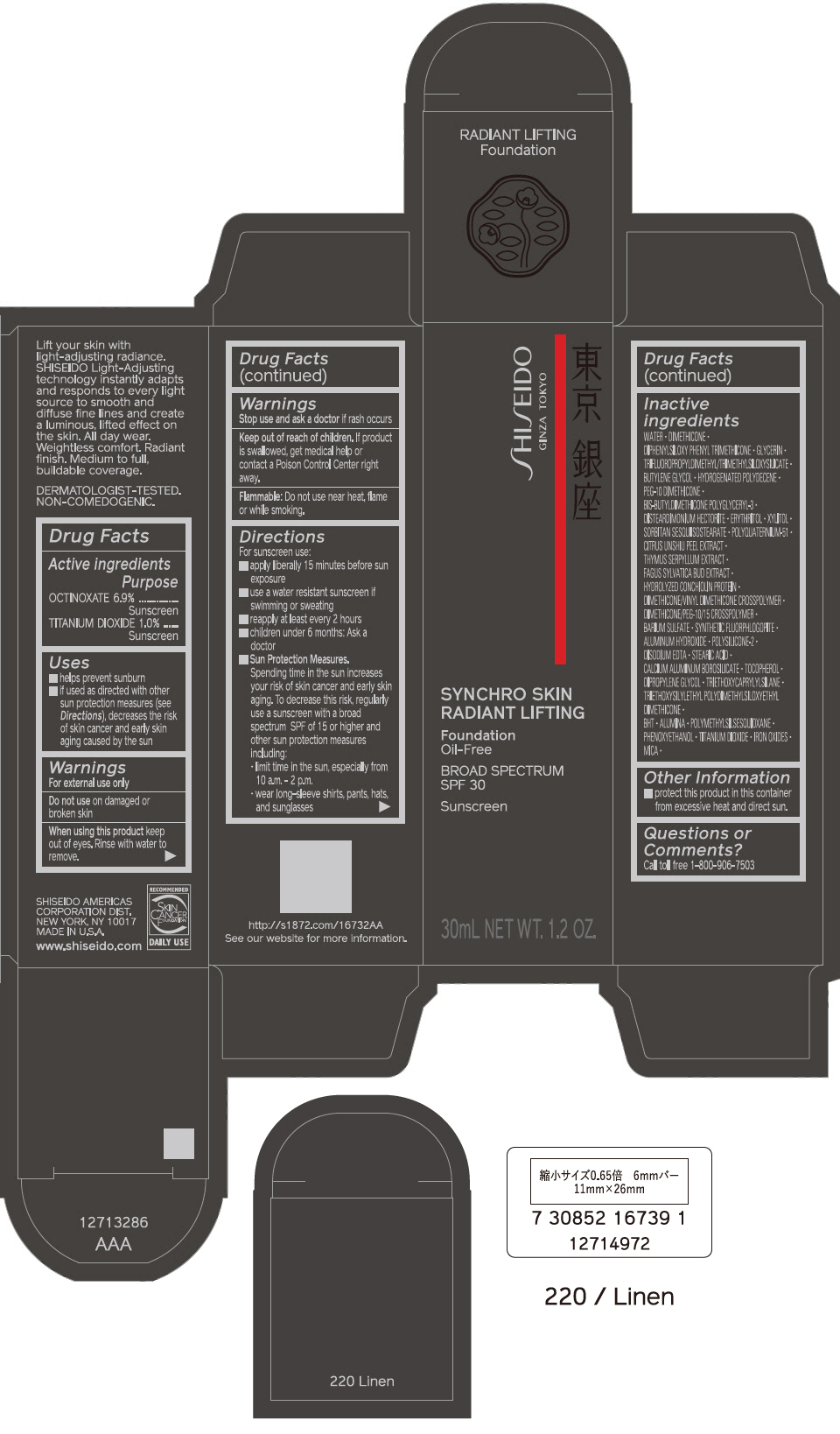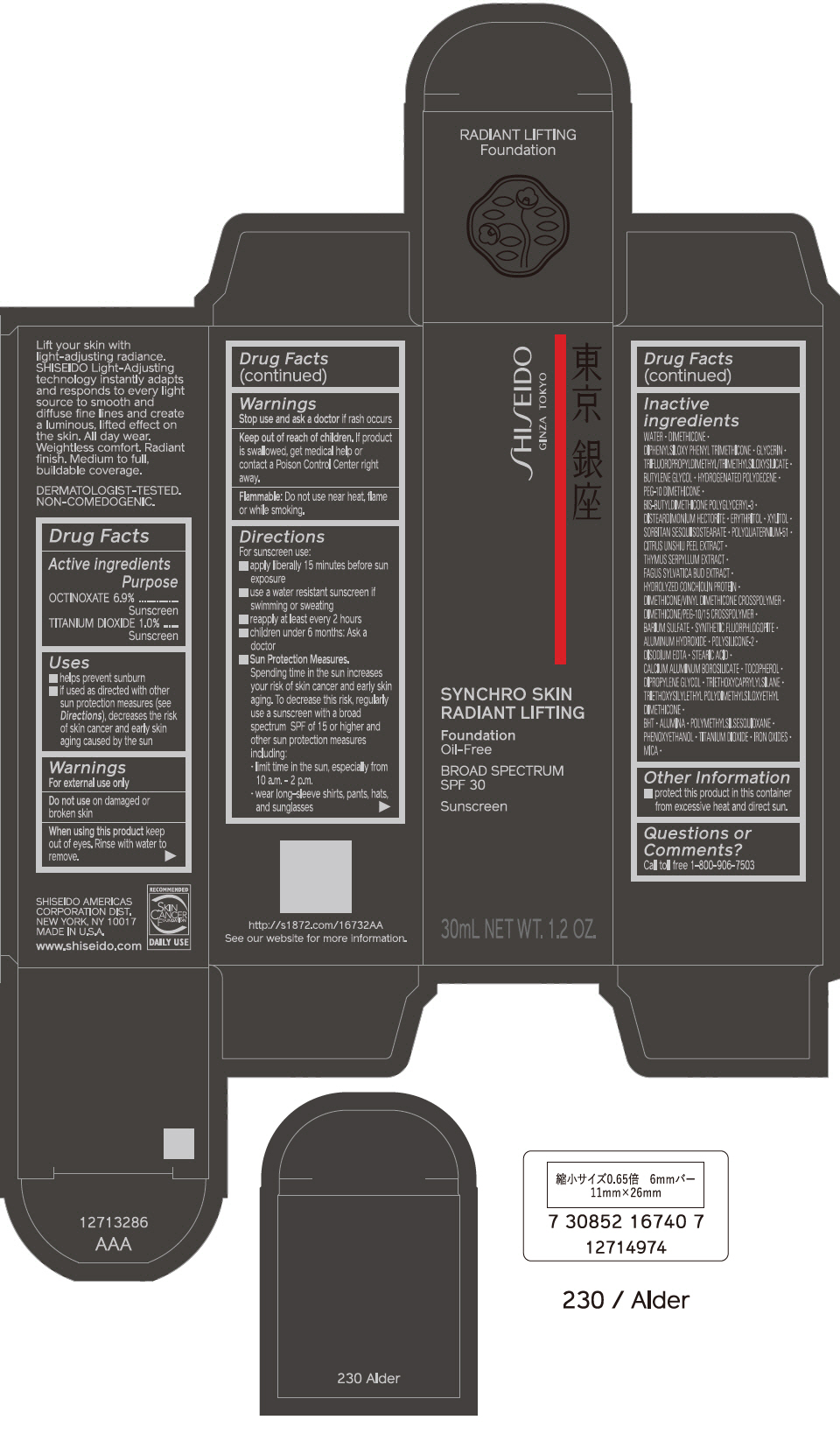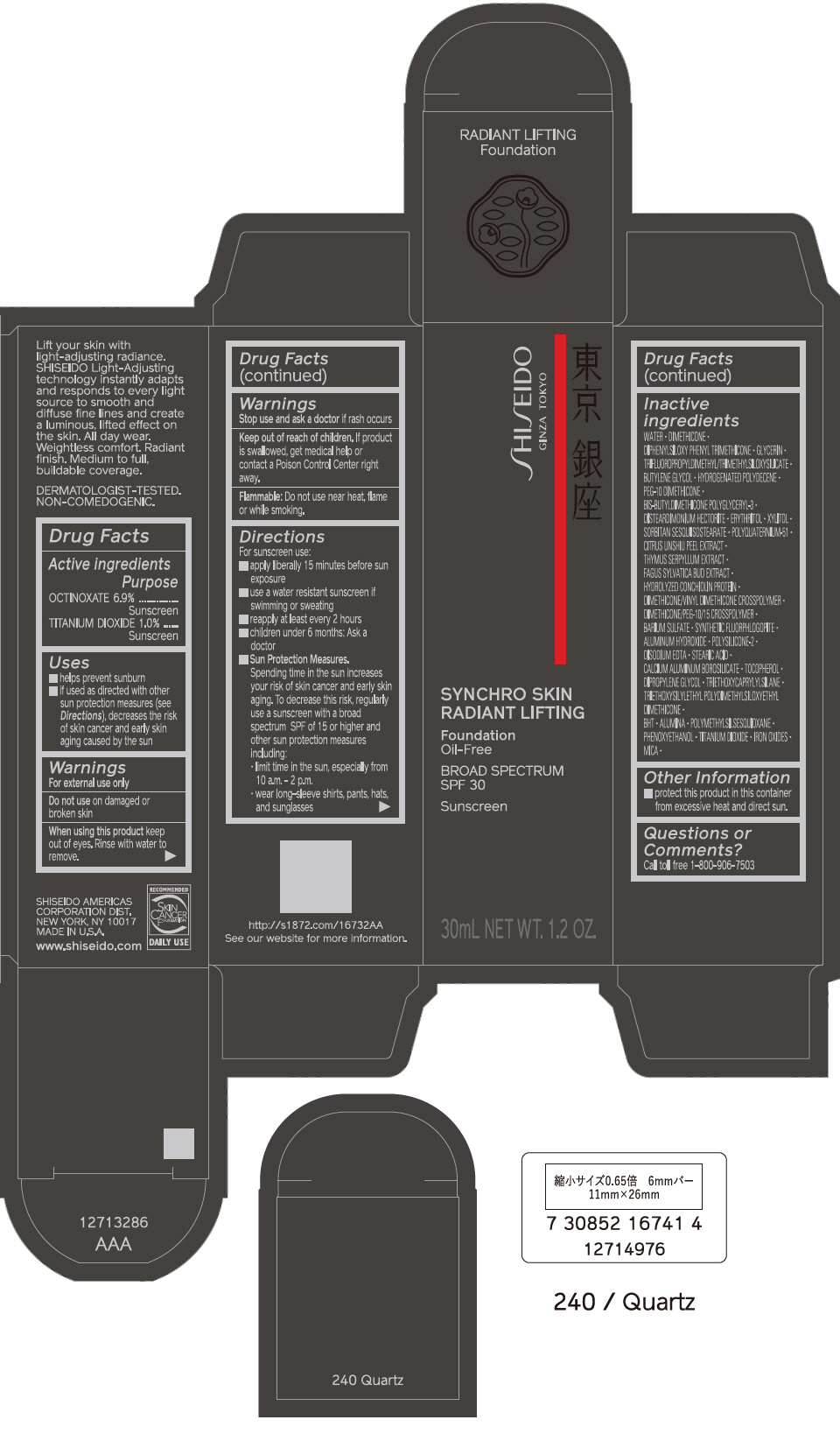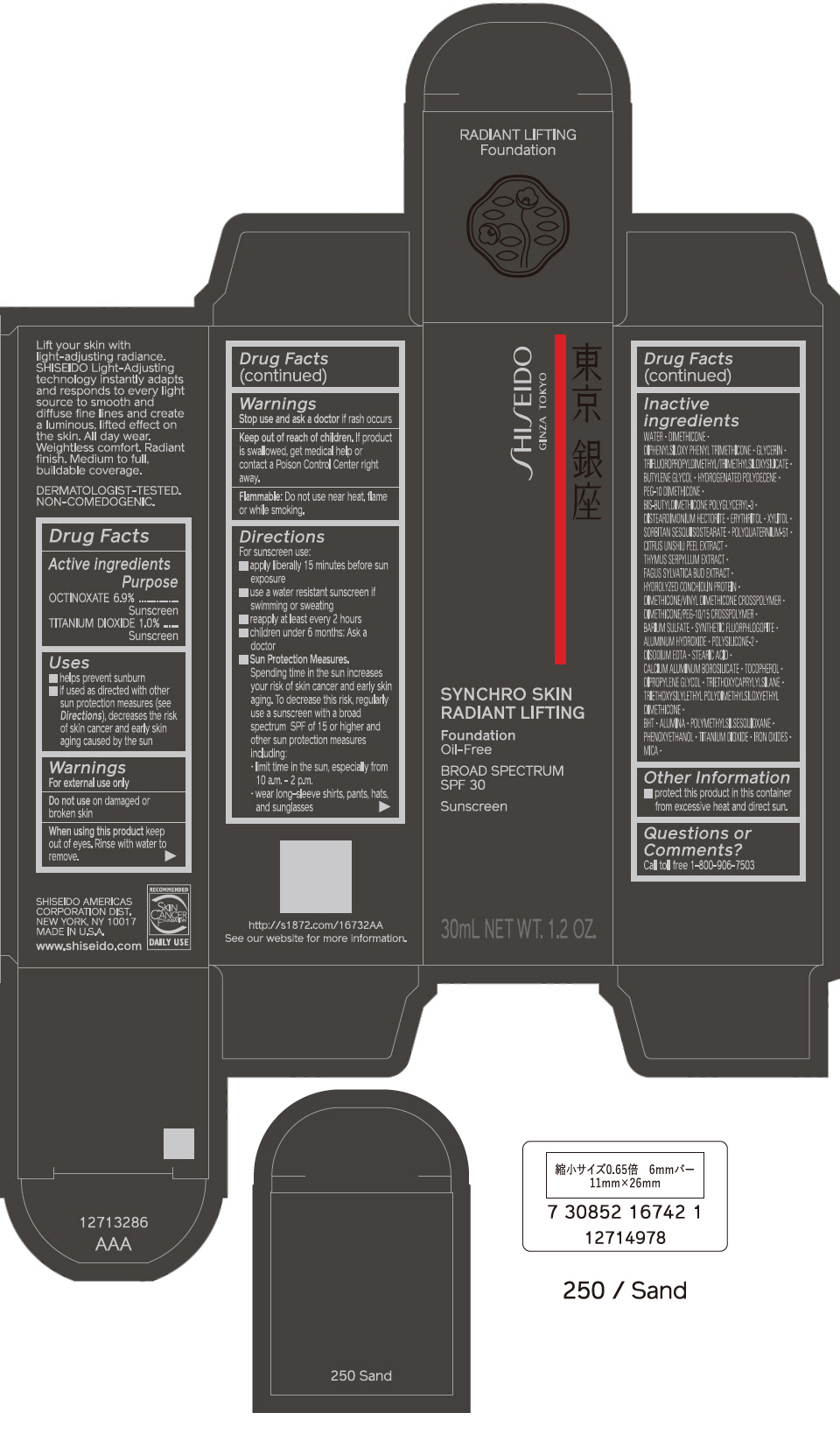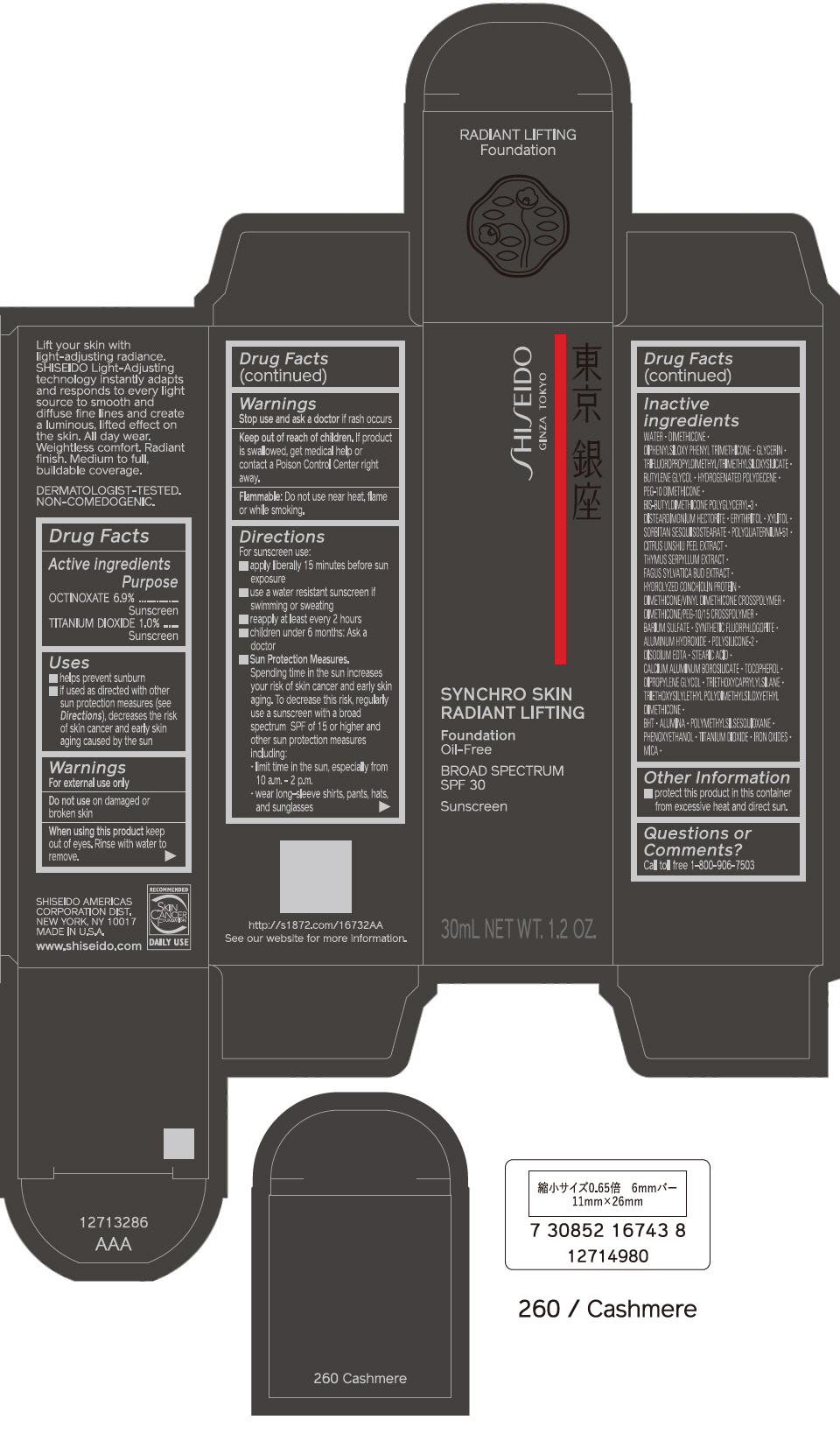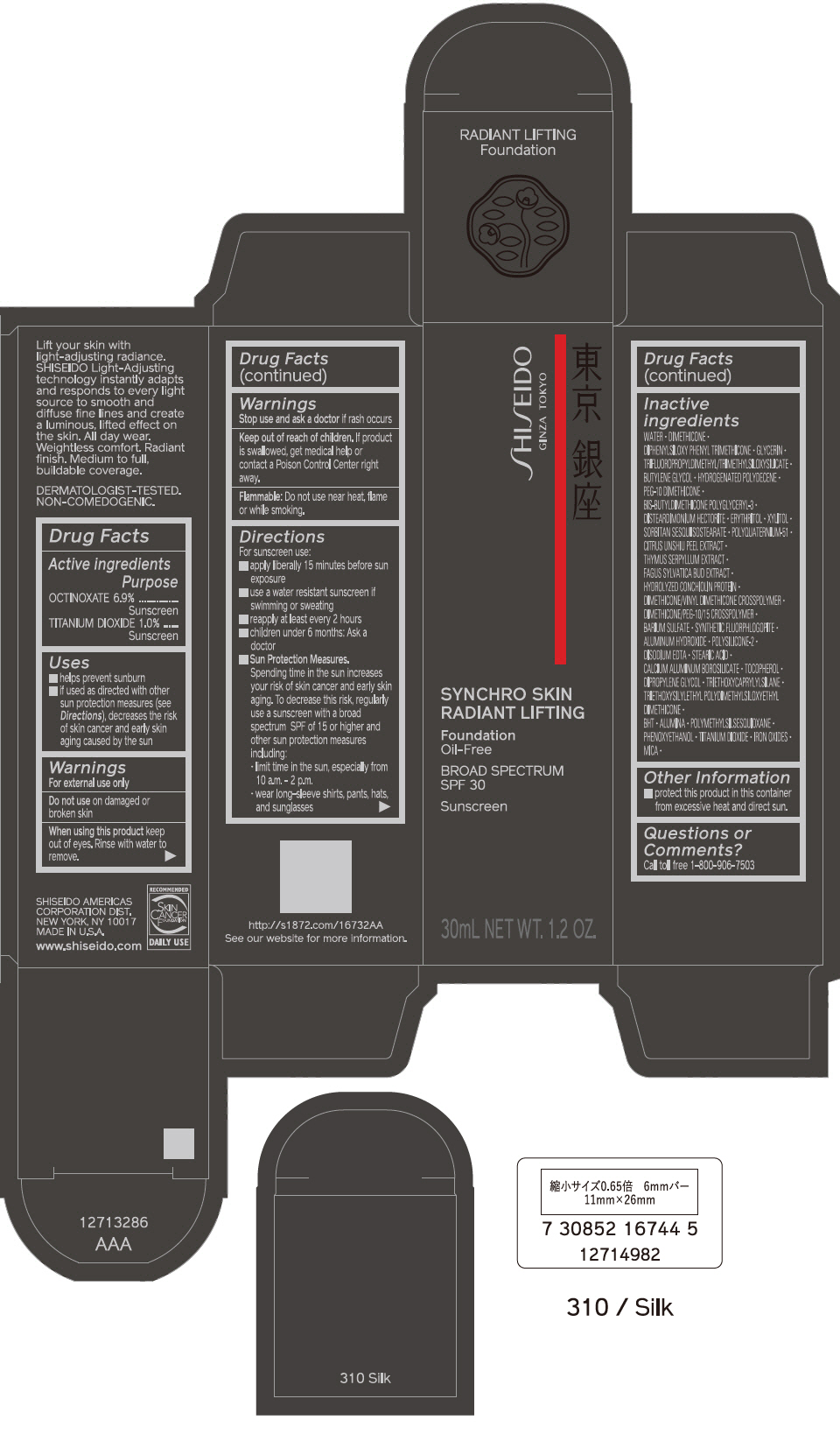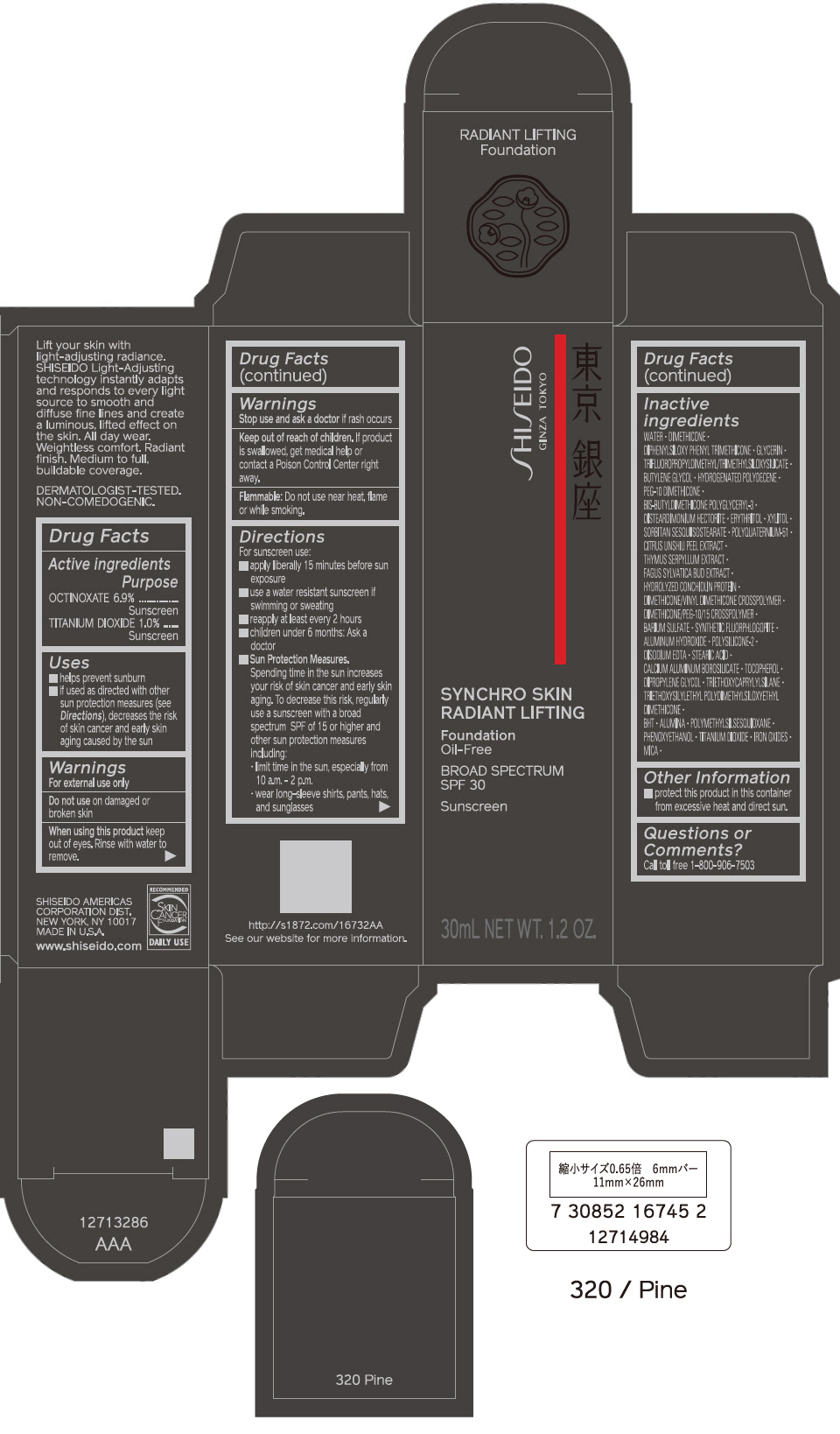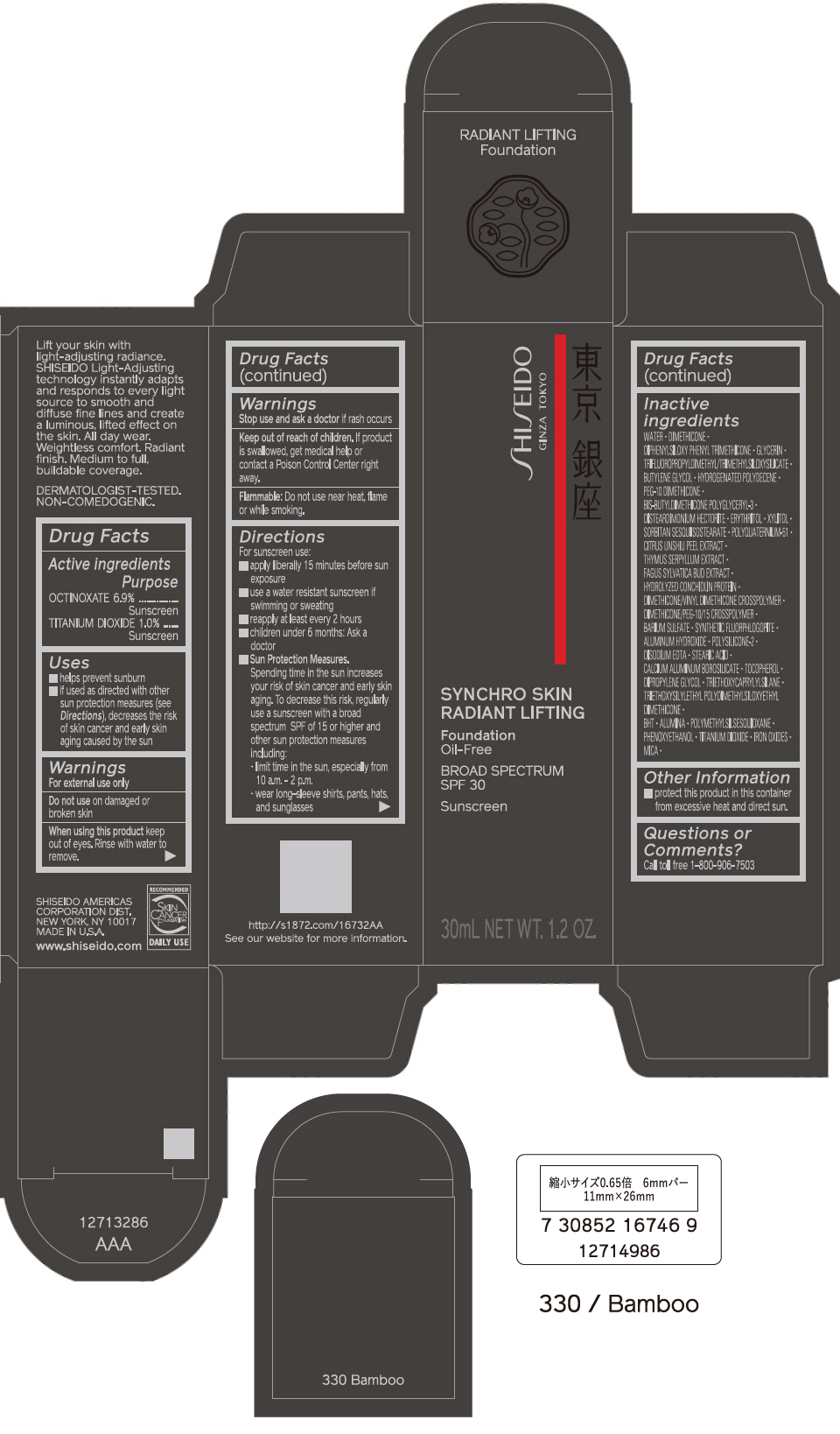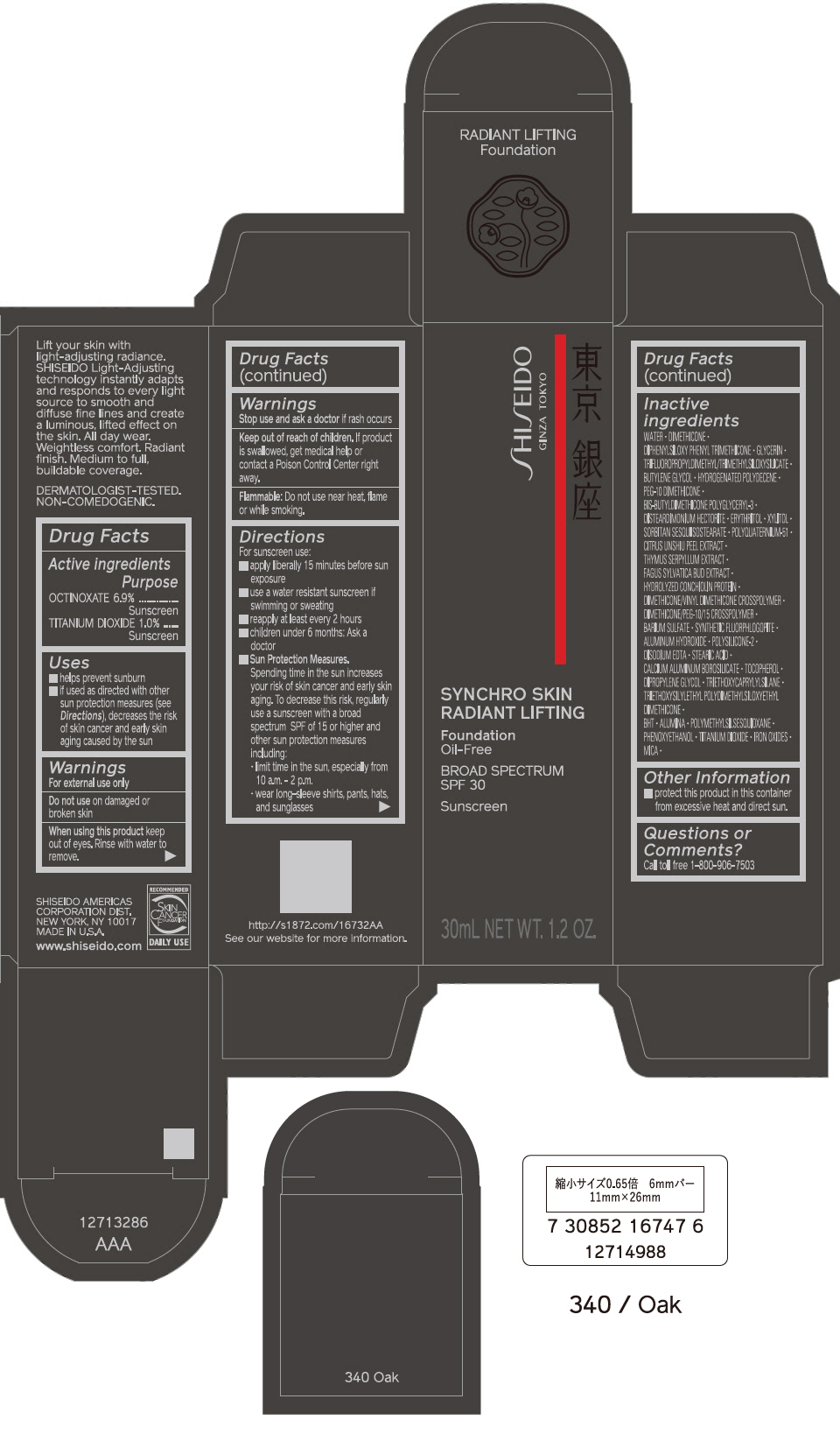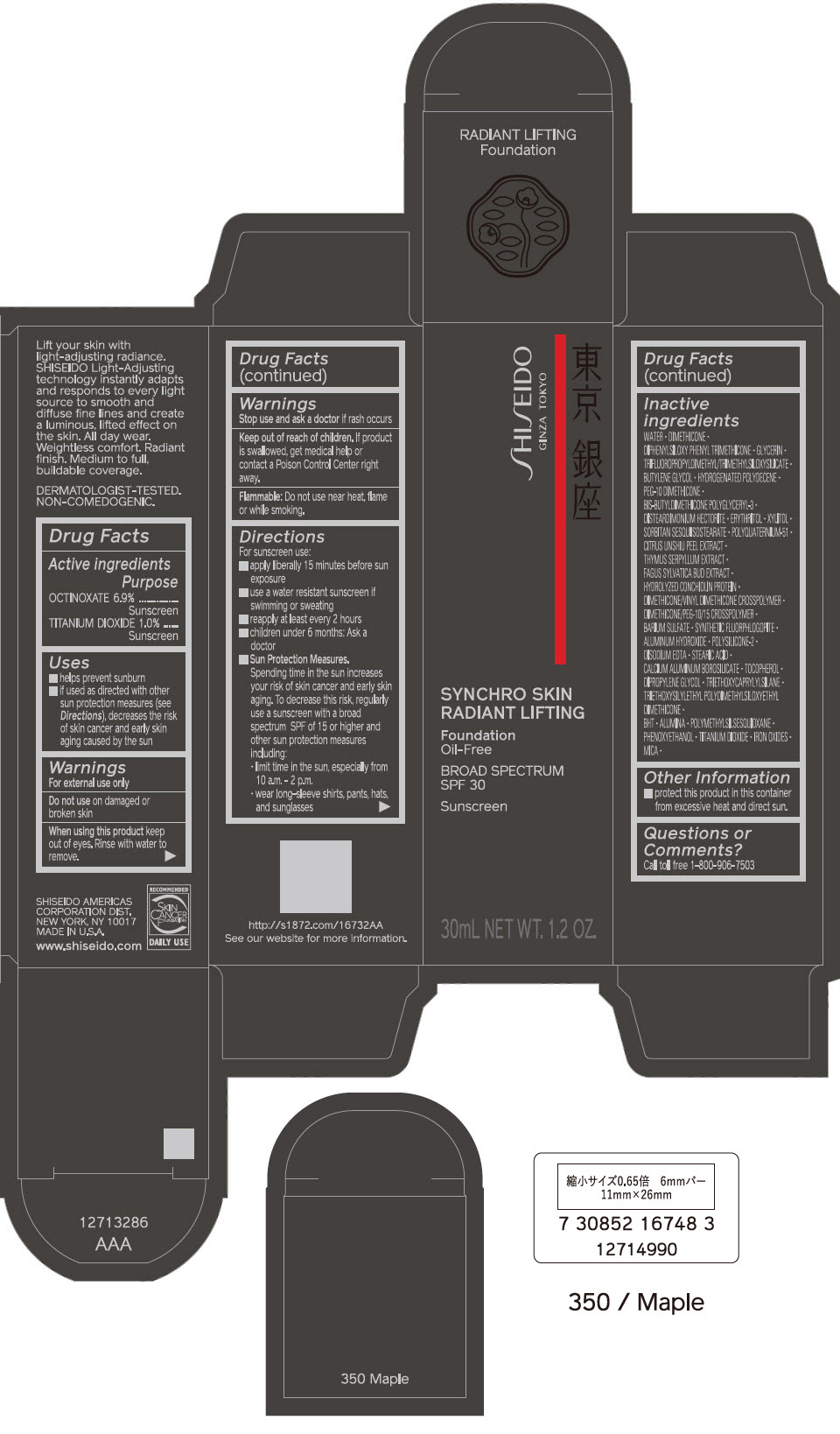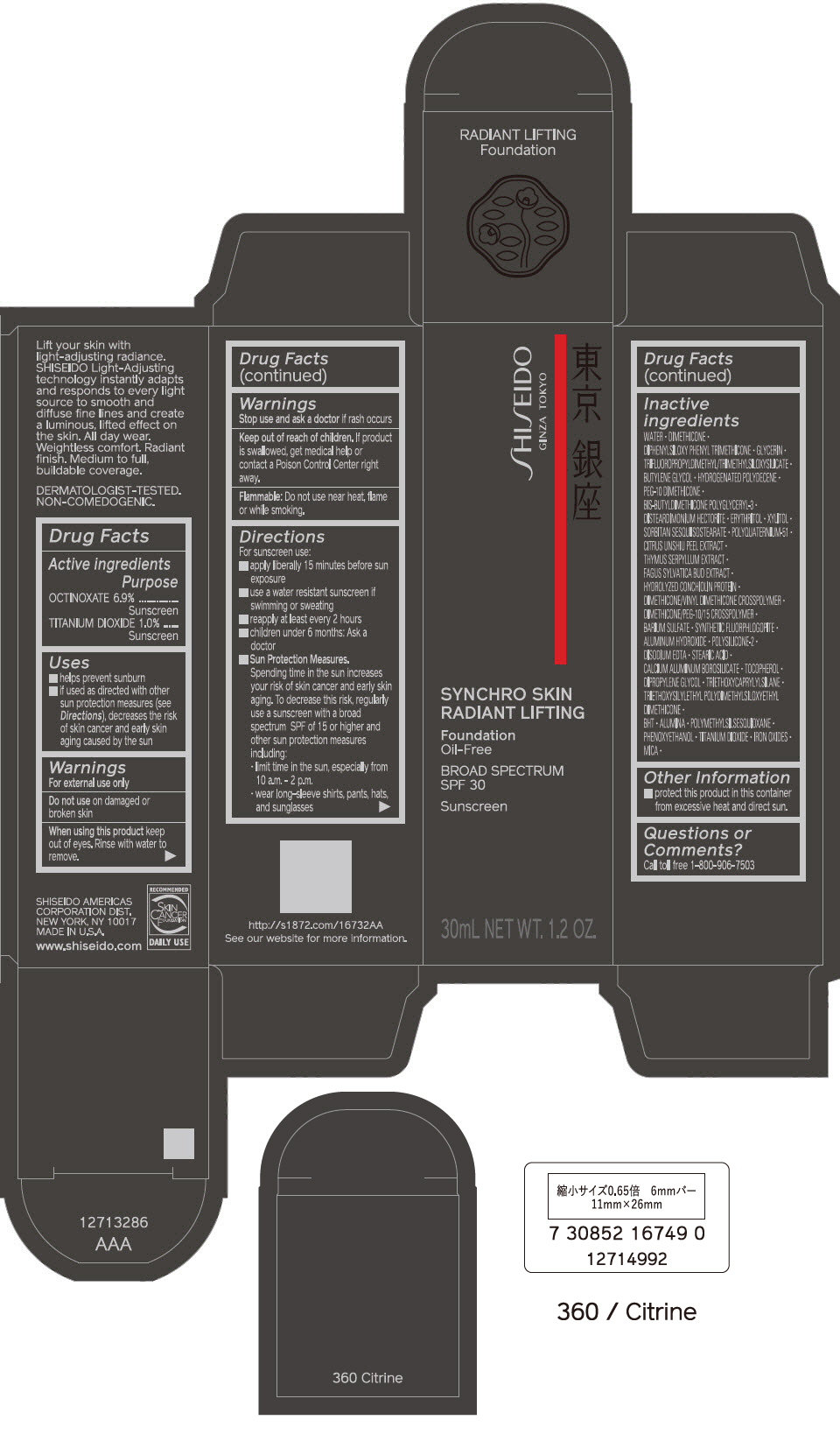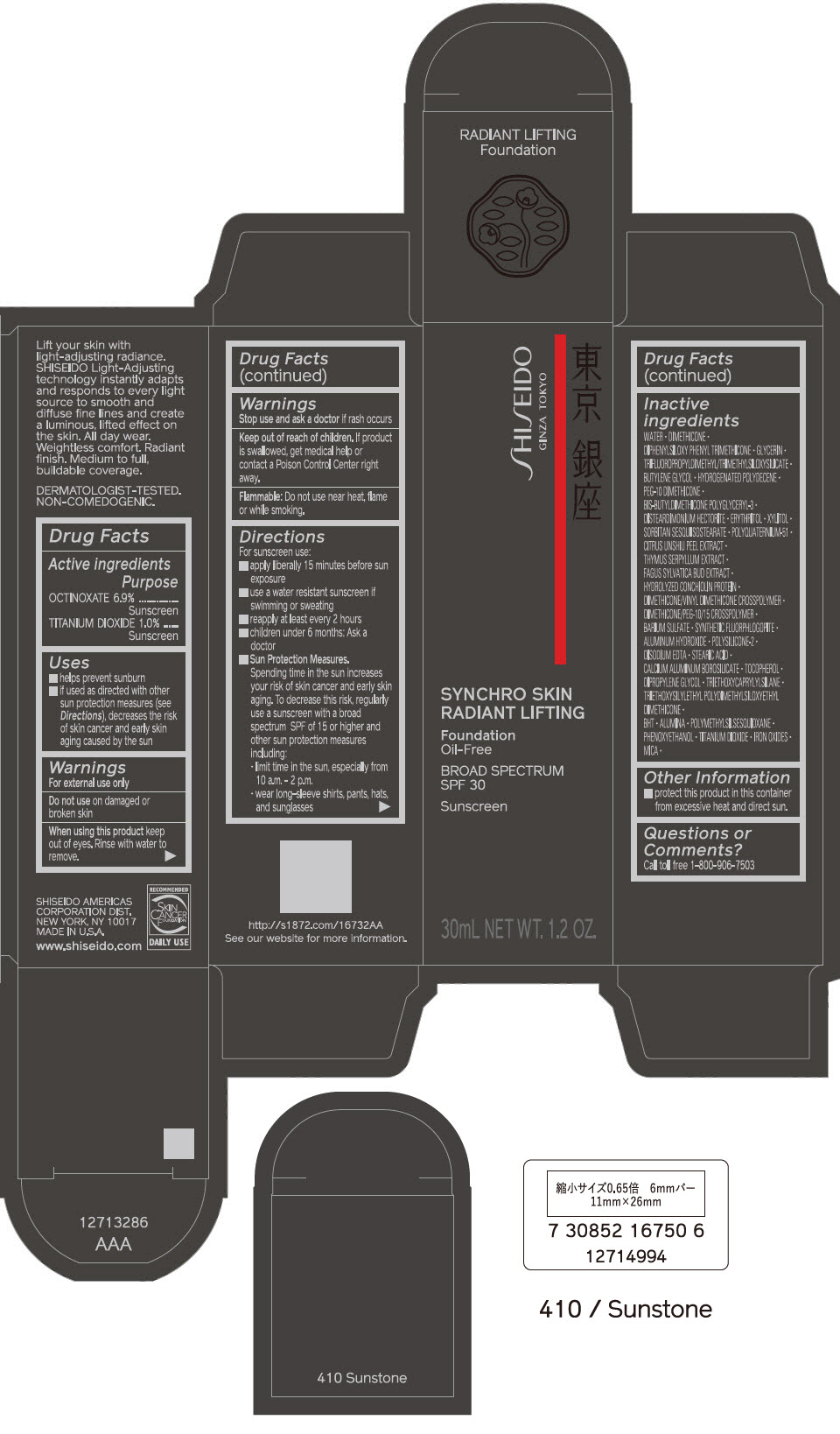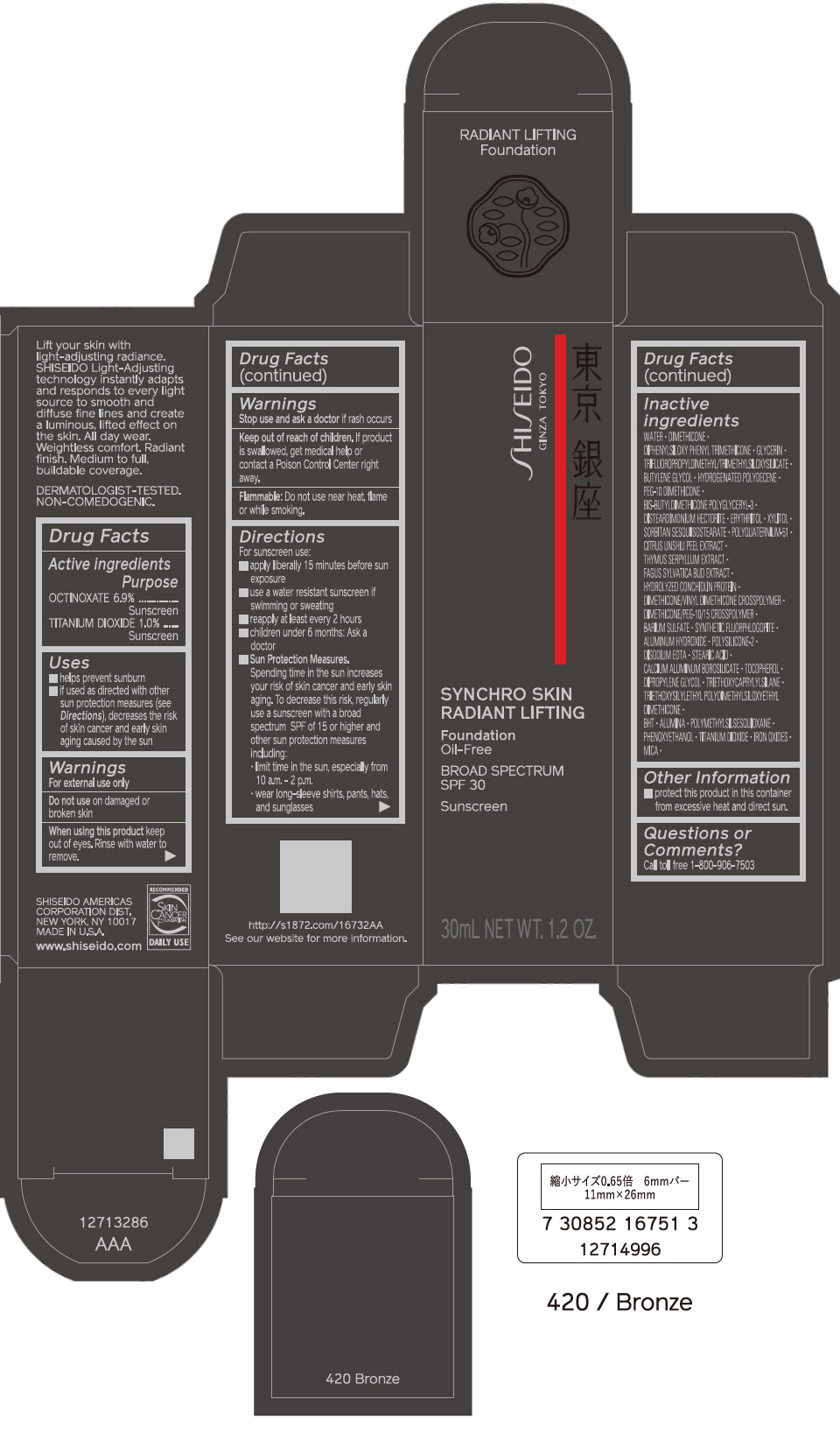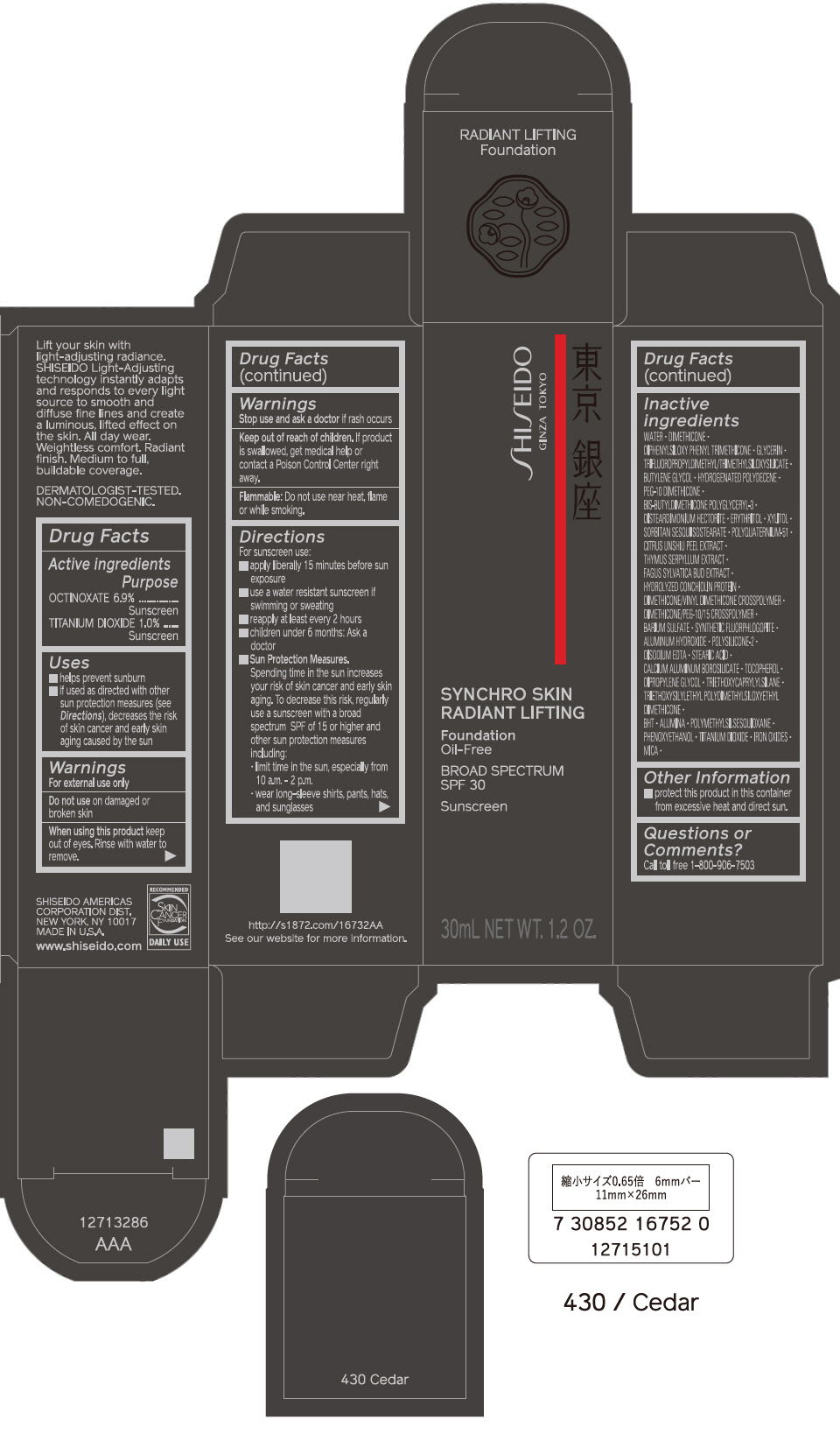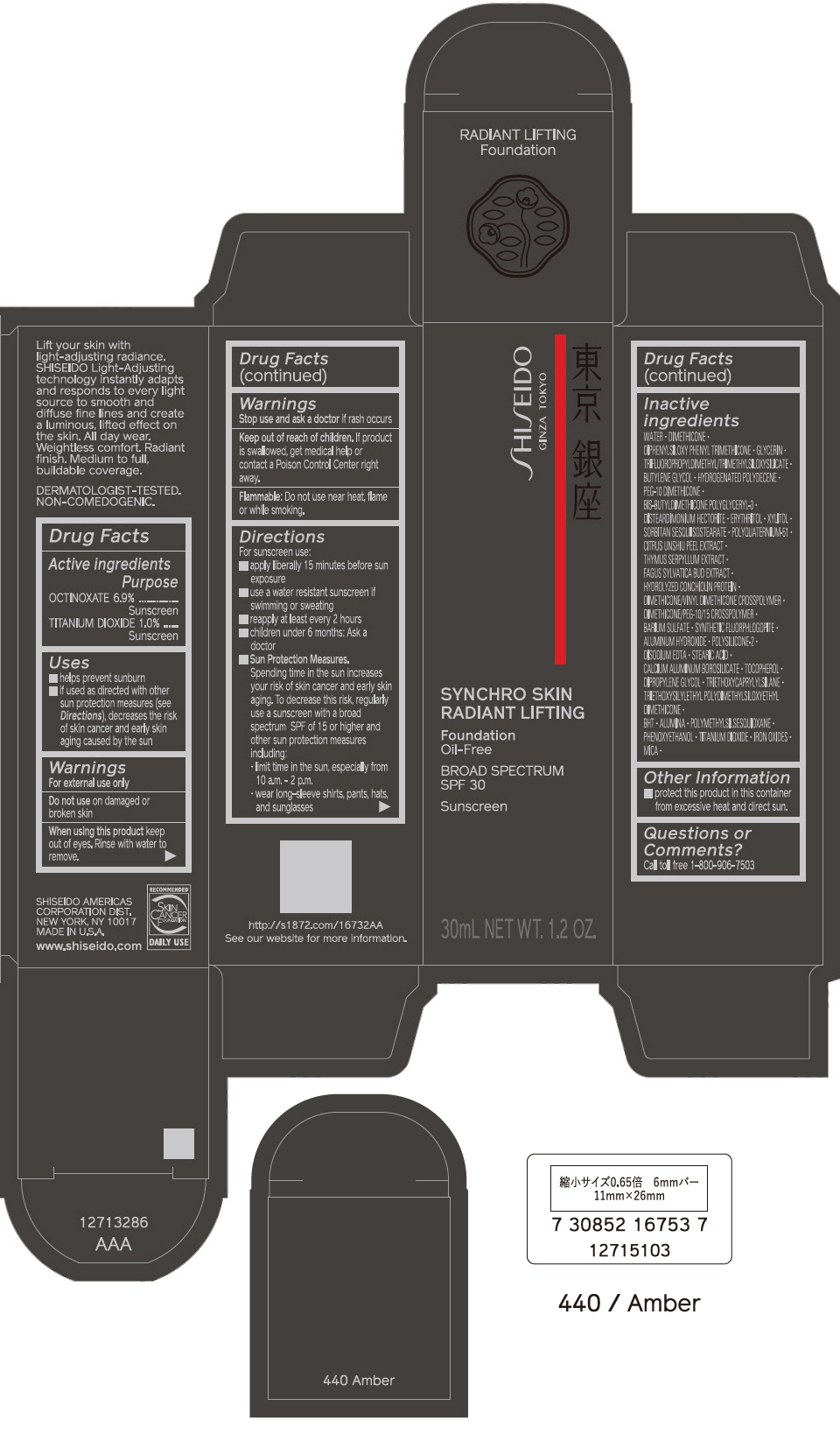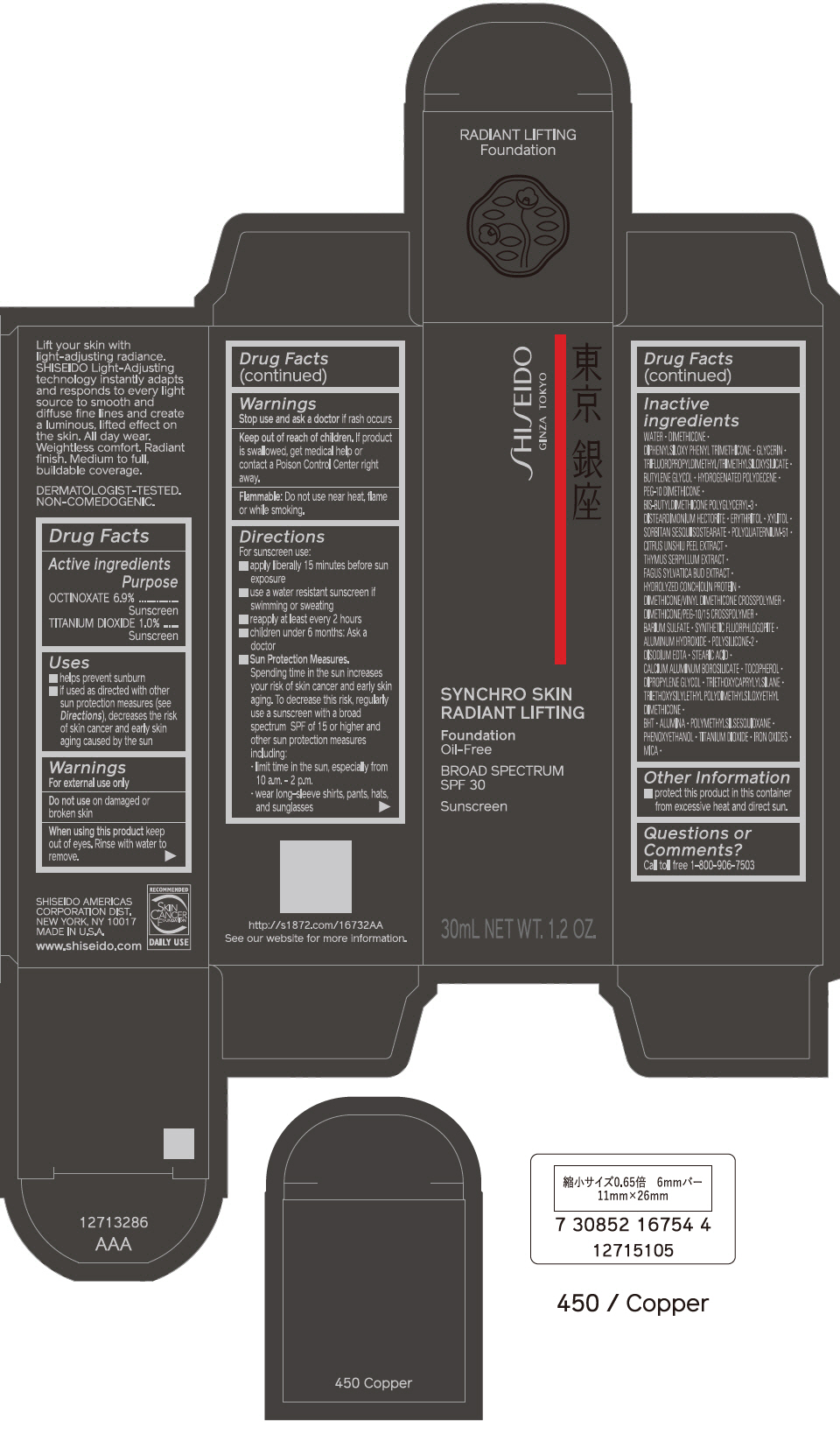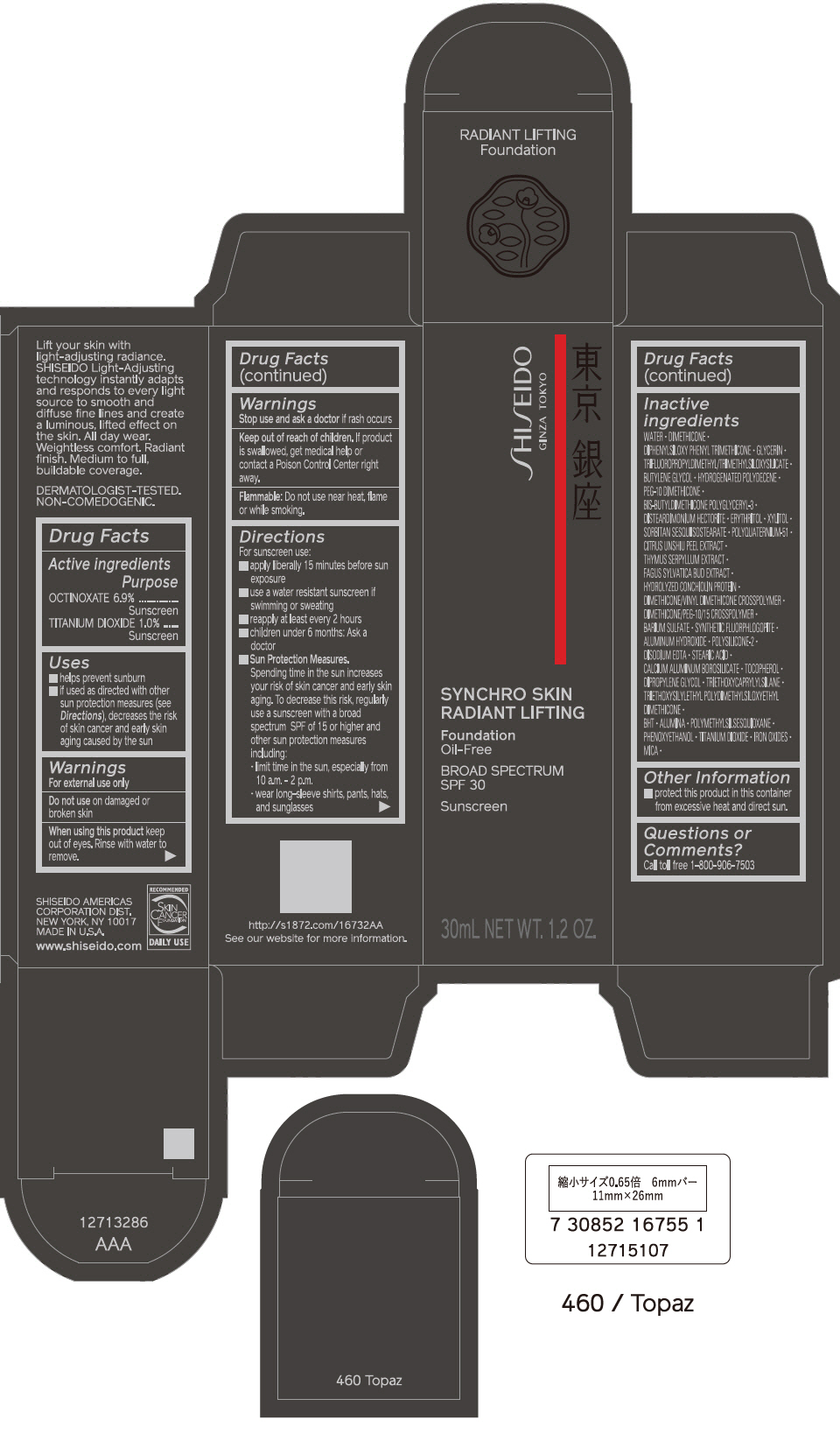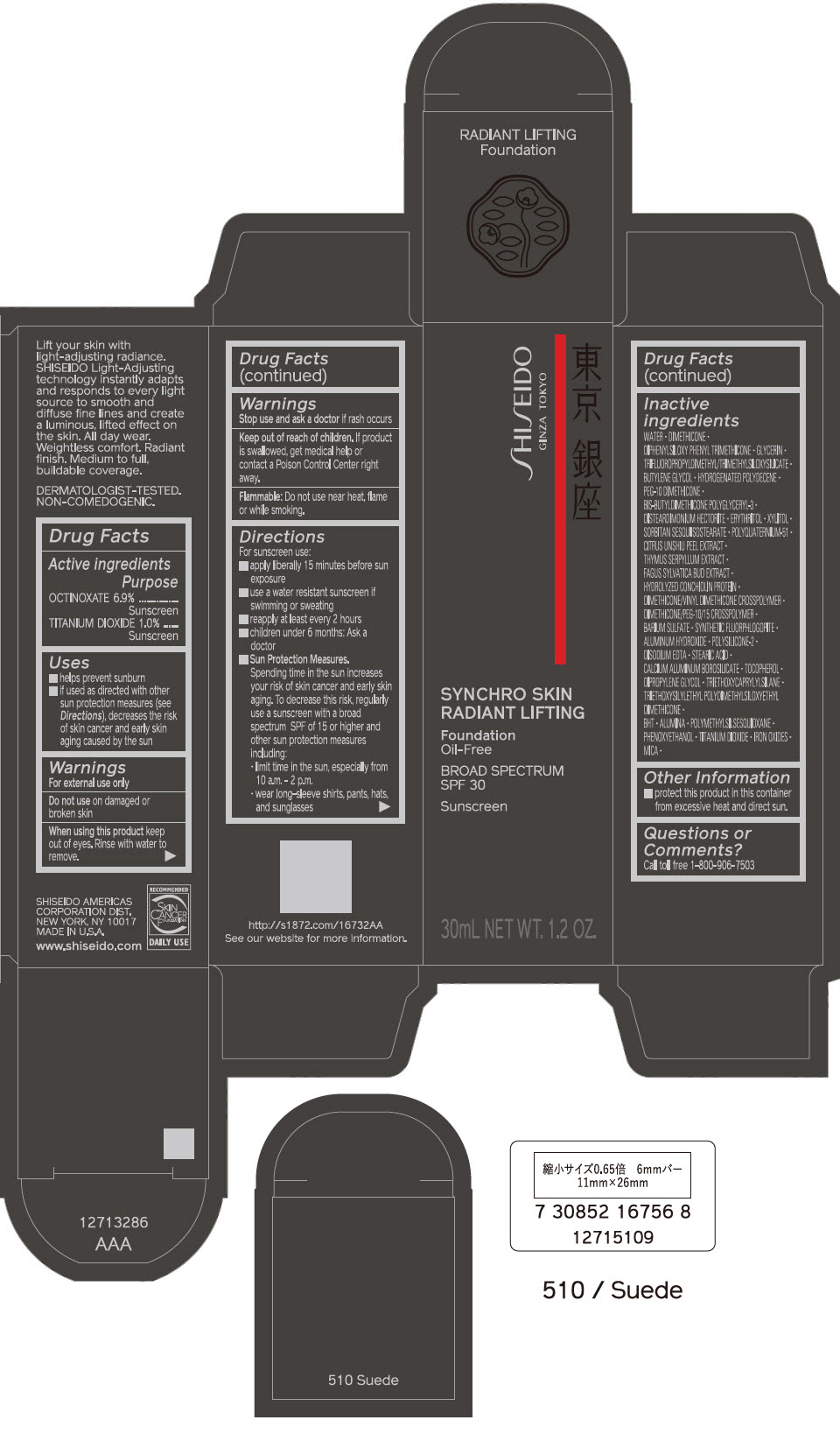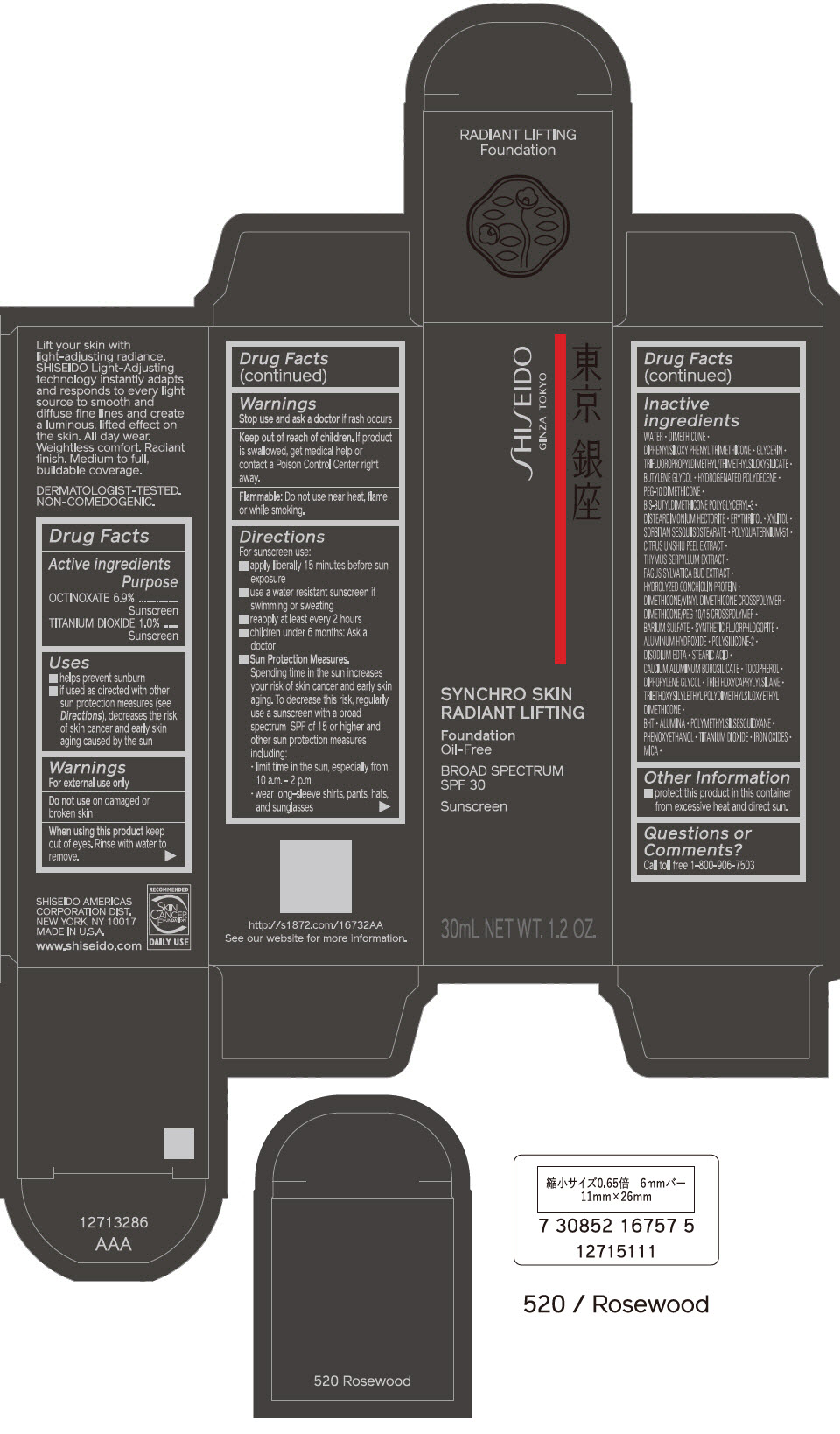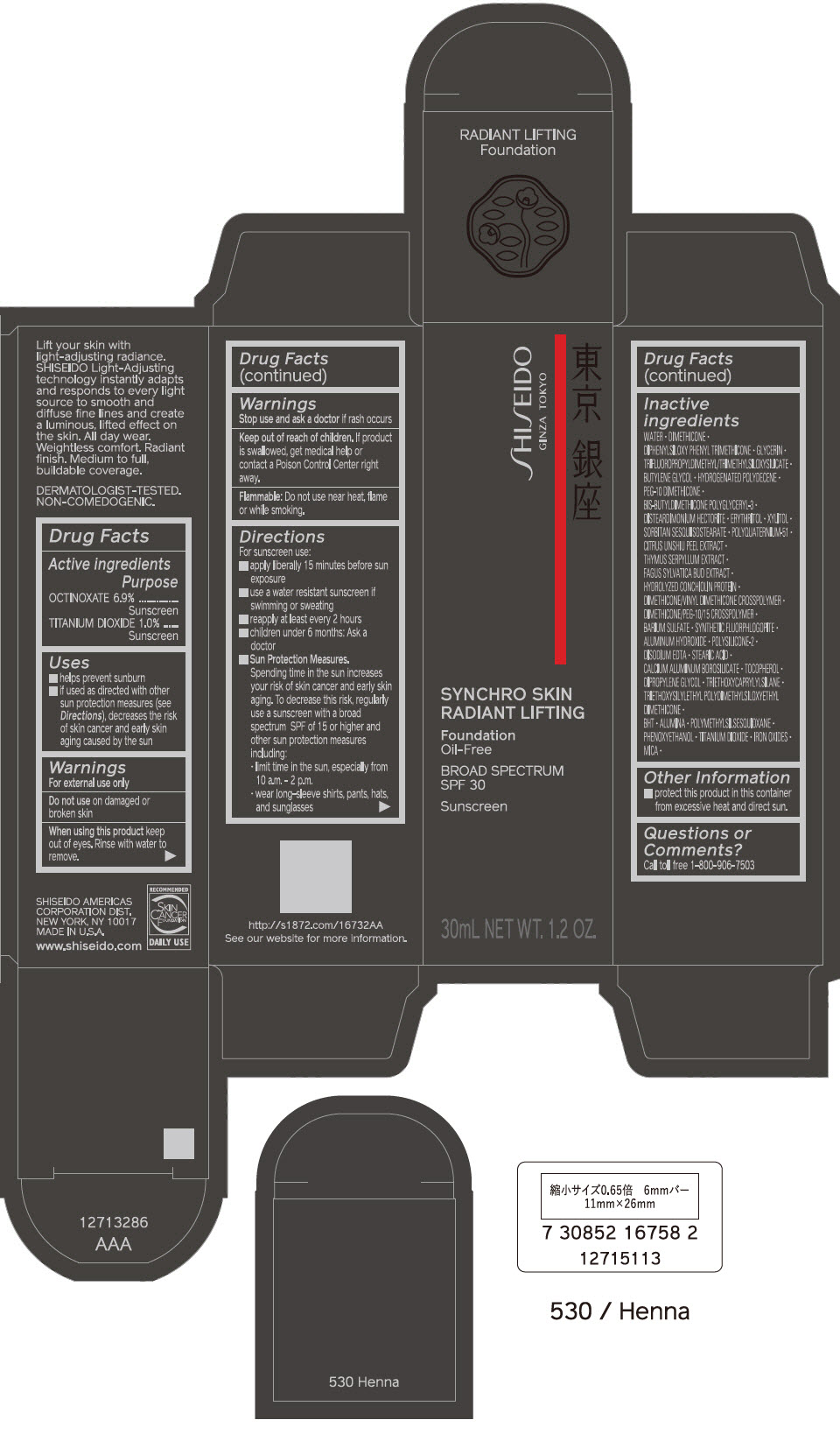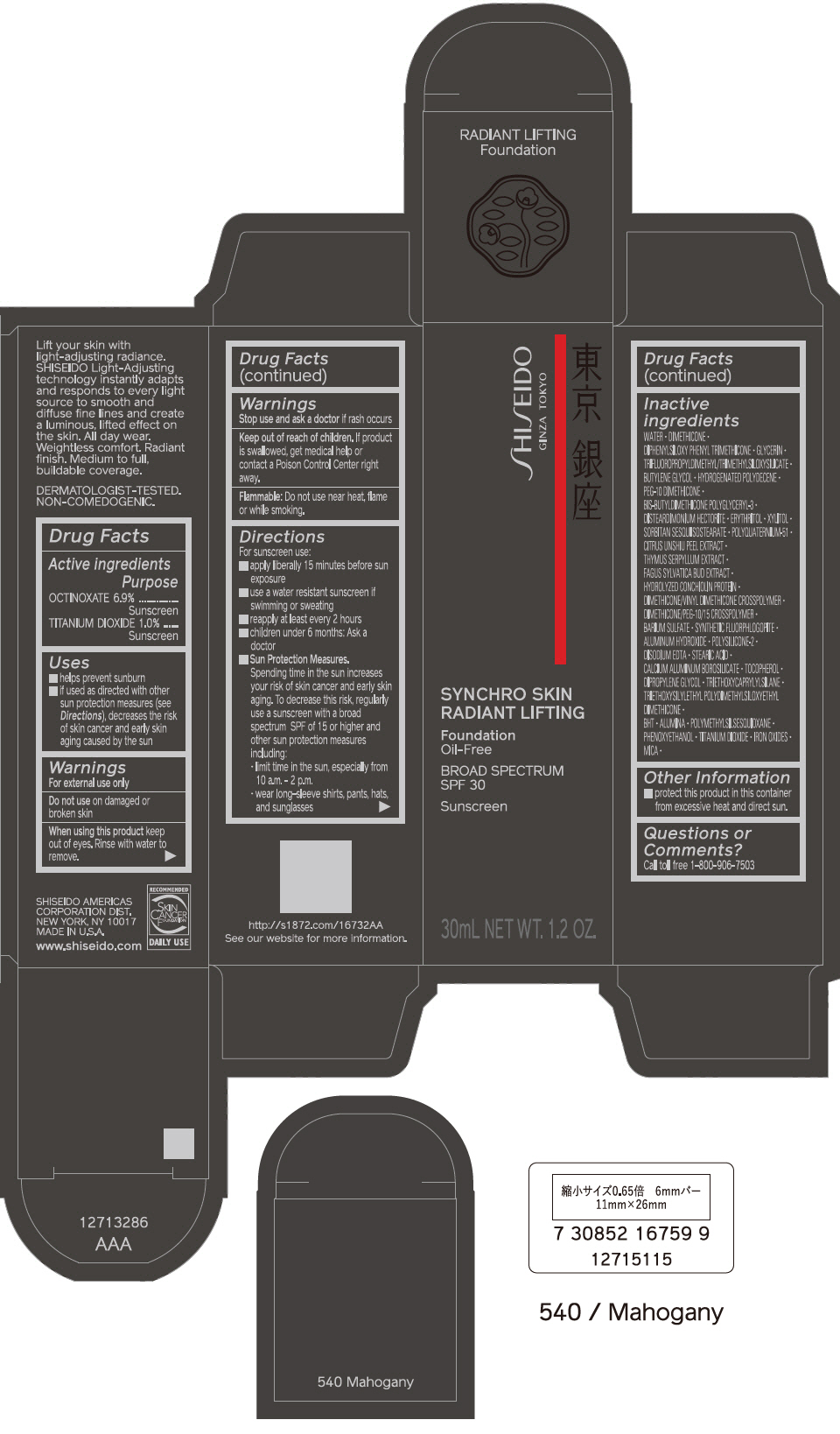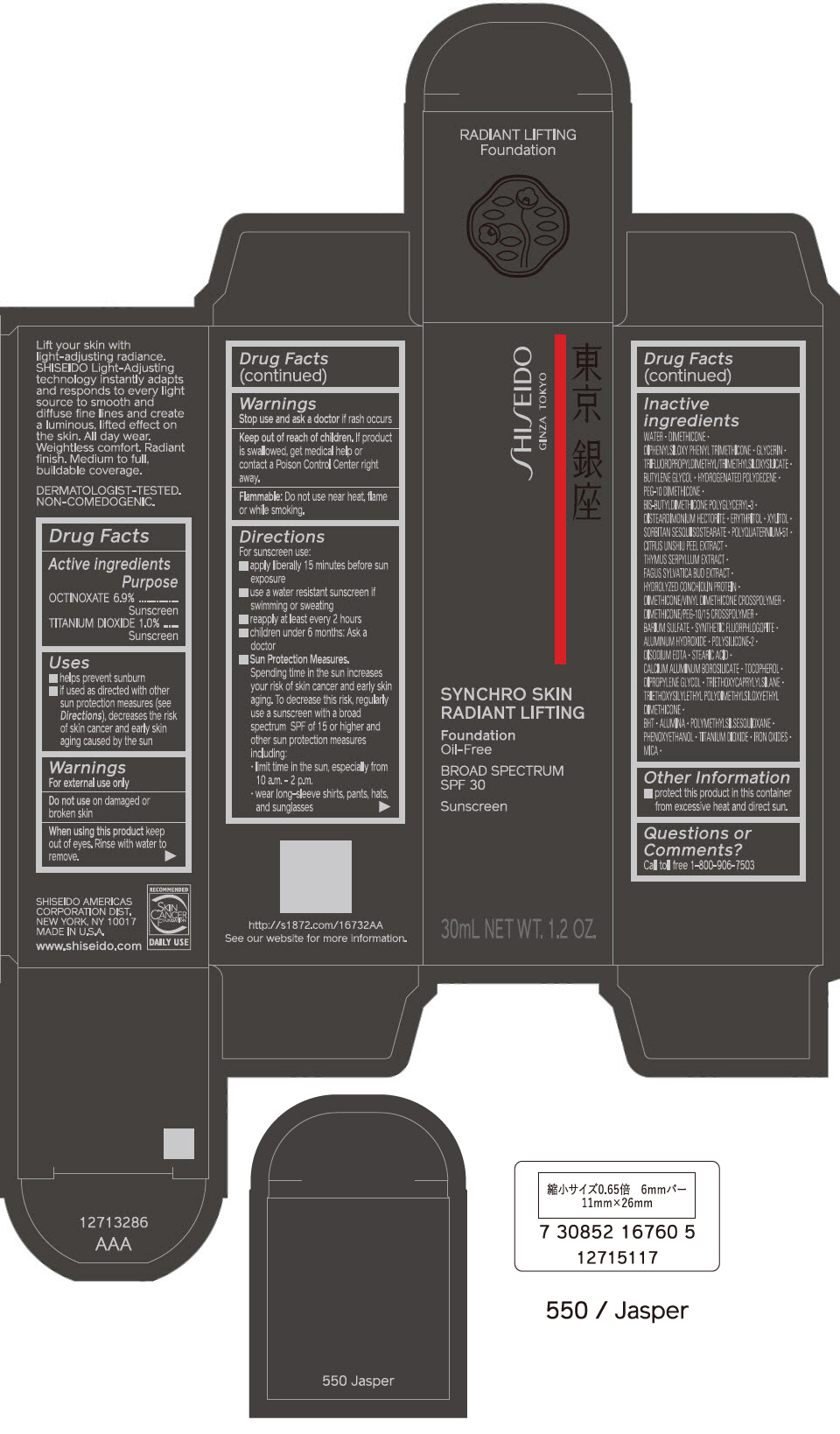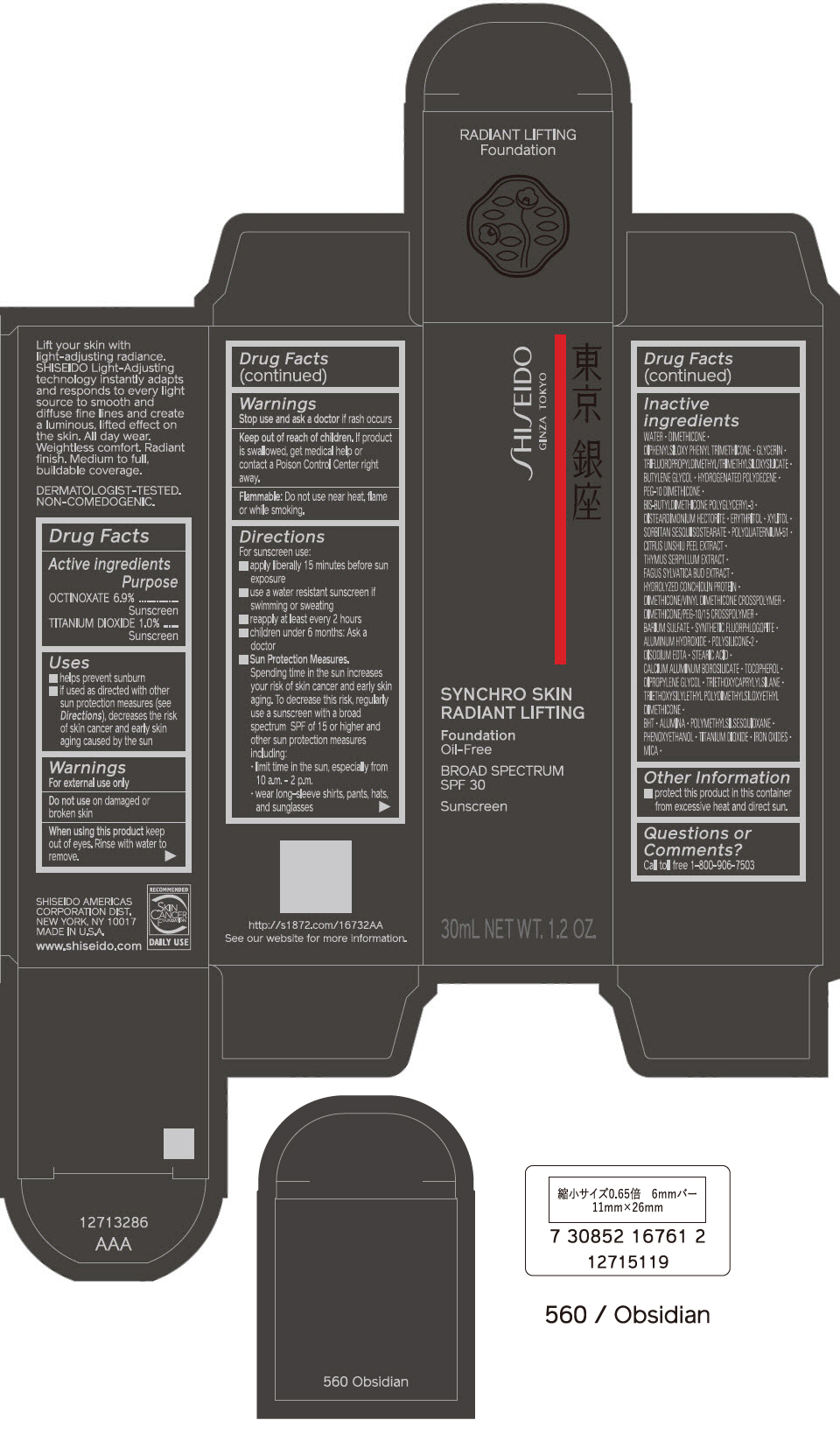 DRUG LABEL: SHISEIDO SYNCHRO SKIN RADIANT LIFTING FOUNDATION 

NDC: 58411-563 | Form: EMULSION
Manufacturer: SHISEIDO AMERICAS CORPORATION
Category: otc | Type: HUMAN OTC DRUG LABEL
Date: 20260105

ACTIVE INGREDIENTS: OCTINOXATE 2.484 g/30 mL; TITANIUM DIOXIDE 0.36 g/30 mL
INACTIVE INGREDIENTS: WATER; DIMETHICONE; DIPHENYLSILOXY PHENYL TRIMETHICONE; GLYCERIN; BUTYLENE GLYCOL; HYDROGENATED POLYDECENE TYPE I; PEG-10 DIMETHICONE (600 CST); DISTEARDIMONIUM HECTORITE; ERYTHRITOL; XYLITOL; SORBITAN SESQUIISOSTEARATE; POLYQUATERNIUM-51 (2-METHACRYLOYLOXYETHYL PHOSPHORYLCHOLINE/N-BUTYL METHACRYLATE; 3:7); TANGERINE PEEL; THYMUS SERPYLLUM WHOLE; FAGUS SYLVATICA FLOWER BUD; DIMETHICONE/VINYL DIMETHICONE CROSSPOLYMER (SOFT PARTICLE); BARIUM SULFATE; ALUMINUM HYDROXIDE; EDETATE DISODIUM; STEARIC ACID; CALCIUM ALUMINUM BOROSILICATE; .ALPHA.-TOCOPHEROL; DIPROPYLENE GLYCOL; TRIETHOXYCAPRYLYLSILANE; BUTYLATED HYDROXYTOLUENE; ALUMINUM OXIDE; POLYMETHYLSILSESQUIOXANE (4.5 MICRONS); PHENOXYETHANOL; FERRIC OXIDE RED; FERRIC OXIDE YELLOW; FERROSOFERRIC OXIDE; MICA

SHISEIDO SYNCHRO SKIN RADIANT LIFTING FOUNDATION

Drug Facts

ACTIVE INGREDIENT

Active ingredients | Purpose
OCTINOXATE 6.9% | Sunscreen
TITANIUM DIOXIDE 1.0% | Sunscreen

Uses

- helps prevent sunburn
- if used as directed with other sun protection measures (see Directions), decreases the risk of skin cancer and early skin aging caused by the sun

Warnings

For external use only

Do not useon damaged or broken skin

WHEN USING

When using this productkeep out of eyes. Rinse with water to remove.

Stop use and ask a doctorif rash occurs.

Keep out of reach of children.If product is swallowed, get medical help or contact a Poison Control Center right away.

Flammable: Do not use near heat, flame or while smoking

Directions

For sunscreen use:

- apply liberally 15 minutes before sun exposure
- use a water resistant sunscreen if swimming or sweating
- reapply at least every 2 hours
- children under 6 months: Ask a doctor
- Sun Protection Measures. Spending time in the sun increases your risk of skin cancer and early skin aging. To decrease this risk, regularly use a sunscreen with a Broad Spectrum SPF of 15 or higher and other un protection measures including:
  - limit time in the sun, especially from 10 a.m. – 2 p.m.
  - wear long-sleeve shirts, pants, hats, and sunglasses

Inactive Ingredients

WATER▪DIMETHICONE▪DIPHENYLSILOXY PHENYL TRIMETHICONE▪GLYCERIN▪TRIFLUOROPROPYLDIMETHYL/TRIMETHYLSILOXYSILICATE▪BUTYLENE GLYCOL▪HYDROGENATED POLYDECENE▪PEG-10 DIMETHICONE▪BIS-BUTYLDIMETHICONE POLYGLYCERYL-3▪DISTEARDIMONIUM HECTORITE▪ERYTHRITOL▪XYLITOL▪SORBITAN SESQUIISOSTEARATE▪POLYQUATERNIUM-51▪CITRUS UNSHIU PEEL EXTRACT▪THYMUS SERPYLLUM EXTRACT▪FAGUS SYLVATICA BUD EXTRACT▪HYDROLYZED CONCHIOLIN PROTEIN▪DIMETHICONE/VINYL DIMETHICONE CROSSPOLYMER▪DIMETHICONE/PEG-10/15 CROSSPOLYMER▪BARIUM SULFATE▪SYNTHETIC FLUORPHLOGOPITE▪ALUMINUM HYDROXIDE▪POLYSILICONE-2▪DISODIUM EDTA�STEARIC ACID▪CALCIUM ALUMINUM BOROSILICATE▪TOCOPHEROL▪DIPROPYLENE GLYCOL▪TRIETHOXYCAPRYLYLSILANE▪TRIETHOXYSILYLETHYL POLYDIMETHYLSILOXYETHYL DIMETHICONE▪BHT▪ALUMINA▪POLYMETHYLSILSESQUIOXANE▪PHENOXYETHANOL▪TITANIUM DIOXIDE▪IRON OXIDES▪MICA▪

Other information

- protect this product in this container from excessive heat and direct sun.

Questions or comments?

Call toll free 1-800-906-7503

PRINCIPAL DISPLAY PANEL - 30 mL Bottle Carton - 110 Alabaster

SHISEIDO
GINZA TOKYO

SYNCHRO SKIN
RADIANT LIFTING

Foundation
Oil-Free

BROAD SPECTRUM
SPF 30

Sunscreen

30mL NET WT. 1.2 OZ.

PRINCIPAL DISPLAY PANEL - 30 mL Bottle Carton - 120 Ivory

SHISEIDO
GINZA TOKYO

SYNCHRO SKIN
RADIANT LIFTING

Foundation
Oil-Free

BROAD SPECTRUM
SPF 30

Sunscreen

30mL NET WT. 1.2 OZ.

PRINCIPAL DISPLAY PANEL - 30 mL Bottle Carton - 130 Opal

SHISEIDO
GINZA TOKYO

SYNCHRO SKIN
RADIANT LIFTING

Foundation
Oil-Free

BROAD SPECTRUM
SPF 30

Sunscreen

30mL NET WT. 1.2 OZ.

PRINCIPAL DISPLAY PANEL - 30 mL Bottle Carton - 140 Porcelain

SHISEIDO
GINZA TOKYO

SYNCHRO SKIN
RADIANT LIFTING

Foundation
Oil-Free

BROAD SPECTRUM
SPF 30

Sunscreen

30mL NET WT. 1.2 OZ.

PRINCIPAL DISPLAY PANEL - 30 mL Bottle Carton - 150 Lace

SHISEIDO
GINZA TOKYO

SYNCHRO SKIN
RADIANT LIFTING

Foundation
Oil-Free

BROAD SPECTRUM
SPF 30

Sunscreen

30mL NET WT. 1.2 OZ.

PRINCIPAL DISPLAY PANEL - 30 mL Bottle Carton - 160 Shell

SHISEIDO
GINZA TOKYO

SYNCHRO SKIN
RADIANT LIFTING

Foundation
Oil-Free

BROAD SPECTRUM
SPF 30

Sunscreen

30mL NET WT. 1.2 OZ.

PRINCIPAL DISPLAY PANEL - 30 mL Bottle Carton - 210 Birch

SHISEIDO
GINZA TOKYO

SYNCHRO SKIN
RADIANT LIFTING

Foundation
Oil-Free

BROAD SPECTRUM
SPF 30

Sunscreen

30mL NET WT. 1.2 OZ.

PRINCIPAL DISPLAY PANEL - 30 mL Bottle Carton - 220 Linen

SHISEIDO
GINZA TOKYO

SYNCHRO SKIN
RADIANT LIFTING

Foundation
Oil-Free

BROAD SPECTRUM
SPF 30

Sunscreen

30mL NET WT. 1.2 OZ.

PRINCIPAL DISPLAY PANEL - 30 mL Bottle Carton - 230 Alder

SHISEIDO
GINZA TOKYO

SYNCHRO SKIN
RADIANT LIFTING

Foundation
Oil-Free

BROAD SPECTRUM
SPF 30

Sunscreen

30mL NET WT. 1.2 OZ.

PRINCIPAL DISPLAY PANEL - 30 mL Bottle Carton - 240 Quartz

SHISEIDO
GINZA TOKYO

SYNCHRO SKIN
RADIANT LIFTING

Foundation
Oil-Free

BROAD SPECTRUM
SPF 30

Sunscreen

30mL NET WT. 1.2 OZ.

PRINCIPAL DISPLAY PANEL - 30 mL Bottle Carton - 250 Sand

SHISEIDO
GINZA TOKYO

SYNCHRO SKIN
RADIANT LIFTING

Foundation
Oil-Free

BROAD SPECTRUM
SPF 30

Sunscreen

30mL NET WT. 1.2 OZ.

PRINCIPAL DISPLAY PANEL - 30 mL Bottle Carton - 260 Cashmere

SHISEIDO
GINZA TOKYO

SYNCHRO SKIN
RADIANT LIFTING

Foundation
Oil-Free

BROAD SPECTRUM
SPF 30

Sunscreen

30mL NET WT. 1.2 OZ.

PRINCIPAL DISPLAY PANEL - 30 mL Bottle Carton - 310 Silk

SHISEIDO
GINZA TOKYO

SYNCHRO SKIN
RADIANT LIFTING

Foundation
Oil-Free

BROAD SPECTRUM
SPF 30

Sunscreen

30mL NET WT. 1.2 OZ.

PRINCIPAL DISPLAY PANEL - 30 mL Bottle Carton - 320 Pine

SHISEIDO
GINZA TOKYO

SYNCHRO SKIN
RADIANT LIFTING

Foundation
Oil-Free

BROAD SPECTRUM
SPF 30

Sunscreen

30mL NET WT. 1.2 OZ.

PRINCIPAL DISPLAY PANEL - 30 mL Bottle Carton - 330 Bamboo

SHISEIDO
GINZA TOKYO

SYNCHRO SKIN
RADIANT LIFTING

Foundation
Oil-Free

BROAD SPECTRUM
SPF 30

Sunscreen

30mL NET WT. 1.2 OZ.

PRINCIPAL DISPLAY PANEL - 30 mL Bottle Carton - 340 Oak

SHISEIDO
GINZA TOKYO

SYNCHRO SKIN
RADIANT LIFTING

Foundation
Oil-Free

BROAD SPECTRUM
SPF 30

Sunscreen

30mL NET WT. 1.2 OZ.

PRINCIPAL DISPLAY PANEL - 30 mL Bottle Carton - 350 Maple

SHISEIDO
GINZA TOKYO

SYNCHRO SKIN
RADIANT LIFTING

Foundation
Oil-Free

BROAD SPECTRUM
SPF 30

Sunscreen

30mL NET WT. 1.2 OZ.

PRINCIPAL DISPLAY PANEL - 30 mL Bottle Carton - 360 Citrine

SHISEIDO
GINZA TOKYO

SYNCHRO SKIN
RADIANT LIFTING

Foundation
Oil-Free

BROAD SPECTRUM
SPF 30

Sunscreen

30mL NET WT. 1.2 OZ.

PRINCIPAL DISPLAY PANEL - 30 mL Bottle Carton - 410 Sunstone

SHISEIDO
GINZA TOKYO

SYNCHRO SKIN
RADIANT LIFTING

Foundation
Oil-Free

BROAD SPECTRUM
SPF 30

Sunscreen

30mL NET WT. 1.2 OZ.

PRINCIPAL DISPLAY PANEL - 30 mL Bottle Carton - 420 Bronze

SHISEIDO
GINZA TOKYO

SYNCHRO SKIN
RADIANT LIFTING

Foundation
Oil-Free

BROAD SPECTRUM
SPF 30

Sunscreen

30mL NET WT. 1.2 OZ.

PRINCIPAL DISPLAY PANEL - 30 mL Bottle Carton - 430 Cedar

SHISEIDO
GINZA TOKYO

SYNCHRO SKIN
RADIANT LIFTING

Foundation
Oil-Free

BROAD SPECTRUM
SPF 30

Sunscreen

30mL NET WT. 1.2 OZ.

PRINCIPAL DISPLAY PANEL - 30 mL Bottle Carton - 440 Amber

SHISEIDO
GINZA TOKYO

SYNCHRO SKIN
RADIANT LIFTING

Foundation
Oil-Free

BROAD SPECTRUM
SPF 30

Sunscreen

30mL NET WT. 1.2 OZ.

PRINCIPAL DISPLAY PANEL - 30 mL Bottle Carton - 450 Copper

SHISEIDO
GINZA TOKYO

SYNCHRO SKIN
RADIANT LIFTING

Foundation
Oil-Free

BROAD SPECTRUM
SPF 30

Sunscreen

30mL NET WT. 1.2 OZ.

PRINCIPAL DISPLAY PANEL - 30 mL Bottle Carton - 460 Topaz

SHISEIDO
GINZA TOKYO

SYNCHRO SKIN
RADIANT LIFTING

Foundation
Oil-Free

BROAD SPECTRUM
SPF 30

Sunscreen

30mL NET WT. 1.2 OZ.

PRINCIPAL DISPLAY PANEL - 30 mL Bottle Carton - 510 Suede

SHISEIDO
GINZA TOKYO

SYNCHRO SKIN
RADIANT LIFTING

Foundation
Oil-Free

BROAD SPECTRUM
SPF 30

Sunscreen

30mL NET WT. 1.2 OZ.

PRINCIPAL DISPLAY PANEL - 30 mL Bottle Carton - 520 Rosewood

SHISEIDO
GINZA TOKYO

SYNCHRO SKIN
RADIANT LIFTING

Foundation
Oil-Free

BROAD SPECTRUM
SPF 30

Sunscreen

30mL NET WT. 1.2 OZ.

PRINCIPAL DISPLAY PANEL - 30 mL Bottle Carton - 530 Henna

SHISEIDO
GINZA TOKYO

SYNCHRO SKIN
RADIANT LIFTING

Foundation
Oil-Free

BROAD SPECTRUM
SPF 30

Sunscreen

30mL NET WT. 1.2 OZ.

PRINCIPAL DISPLAY PANEL - 30 mL Bottle Carton - 540 Mahogany

SHISEIDO
GINZA TOKYO

SYNCHRO SKIN
RADIANT LIFTING

Foundation
Oil-Free

BROAD SPECTRUM
SPF 30

Sunscreen

30mL NET WT. 1.2 OZ.

PRINCIPAL DISPLAY PANEL - 30 mL Bottle Carton - 550 Jasper

SHISEIDO
GINZA TOKYO

SYNCHRO SKIN
RADIANT LIFTING

Foundation
Oil-Free

BROAD SPECTRUM
SPF 30

Sunscreen

30mL NET WT. 1.2 OZ.

PRINCIPAL DISPLAY PANEL - 30 mL Bottle Carton - 560 Obsidian

SHISEIDO
GINZA TOKYO

SYNCHRO SKIN
RADIANT LIFTING

Foundation
Oil-Free

BROAD SPECTRUM
SPF 30

Sunscreen

30mL NET WT. 1.2 OZ.